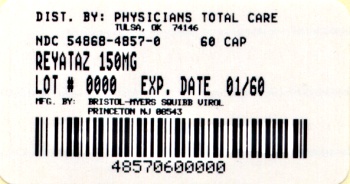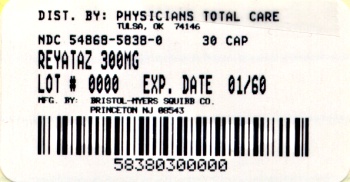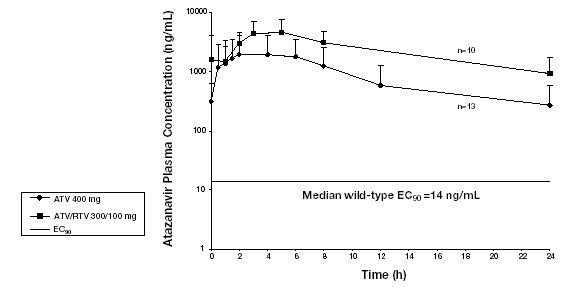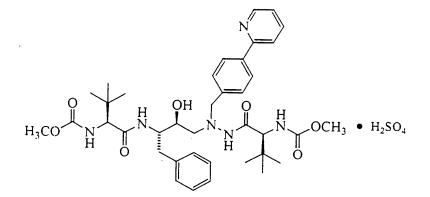 DRUG LABEL: REYATAZ
NDC: 54868-4857 | Form: CAPSULE, GELATIN COATED
Manufacturer: Physicians Total Care, Inc.
Category: prescription | Type: HUMAN PRESCRIPTION DRUG LABEL
Date: 20120217

ACTIVE INGREDIENTS: ATAZANAVIR SULFATE 150 mg/1 1
INACTIVE INGREDIENTS: CROSPOVIDONE; LACTOSE MONOHYDRATE; MAGNESIUM STEARATE; GELATIN; FD&C BLUE NO. 2; TITANIUM DIOXIDE; FERRIC OXIDE RED; FERRIC OXIDE YELLOW; ISOPROPYL ALCOHOL; AMMONIA; PROPYLENE GLYCOL; BUTYL ALCOHOL; ALCOHOL; FERROSOFERRIC OXIDE; SHELLAC

HIGHLIGHTS OF PRESCRIBING INFORMATION

These highlights do not include all the information needed to use REYATAZ safely and effectively. See full prescribing information for REYATAZ.
REYATAZ® (atazanavir sulfate) Capsules
Initial U.S. Approval: 2003

RECENT MAJOR CHANGES

Dosage and Administration (2.2) 10/2011

Dosage and Administration (2.3) 02/2011

1 INDICATIONS AND USAGE

REYATAZ is a protease inhibitor indicated for use in combination with other antiretroviral agents for the treatment of HIV-1 infection. (1)

2 DOSAGE AND ADMINISTRATION

- Treatment-naive patients: REYATAZ 300 mg with ritonavir 100 mg once daily with food or REYATAZ 400 mg once daily with food. When coadministered with tenofovir, the recommended dose is REYATAZ 300 mg with ritonavir 100 mg. (2.1)
- Treatment-experienced patients: REYATAZ 300 mg with ritonavir 100 mg once daily with food. (2.1)
- Pediatric patients (6 to less than 18 years of age): Dosage is based on body weight not to exceed the adult dose. (2.2)
- Pregnancy: REYATAZ 300 mg with ritonavir 100 mg once daily with food, with dosing modifications for some concomitant medications. (2.3)
- Concomitant therapy: Dosing modifications may be required. (2.1, 7)
- Renal impairment: Dosing modifications may be required. (2.4)
- Hepatic impairment: Dosing modifications may be required. (2.5)

3 DOSAGE FORMS AND STRENGTHS

- Capsules: 100 mg, 150 mg, 200 mg, 300 mg. (3, 16)

4 CONTRAINDICATIONS

- REYATAZ is contraindicated in patients with previously demonstrated hypersensitivity (eg, Stevens-Johnson syndrome, erythema multiforme, or toxic skin eruptions) to any of the components of this product. (4)
- Coadministration with alfuzosin, triazolam, orally administered midazolam, ergot derivatives, rifampin, irinotecan, lovastatin, simvastatin, indinavir, cisapride, pimozide, St. John’s wort, and sildenafil when dosed as REVATIO®. (4)

5 WARNINGS AND PRECAUTIONS

- Cardiac conduction abnormalities: PR interval prolongation may occur in some patients. Use with caution in patients with preexisting conduction system disease or when administered with other drugs that may prolong the PR interval. (5.2, 6.4, 7.3, 12.2, 17.3)
- Rash: Discontinue if severe rash develops. (5.3, 6.4, 17.4)
- Hyperbilirubinemia: Most patients experience asymptomatic increases in indirect bilirubin, which is reversible upon discontinuation. Do not dose reduce. If a concomitant transaminase increase occurs, evaluate for alternative etiologies. (5.4, 6.2)
- Hepatotoxicity: REYATAZ should be used with caution in patients with hepatic impairment (5.5). Patients with hepatitis B or C infection are at risk of increased transaminases or hepatic decompensation. Monitor hepatic laboratory tests prior to therapy and during treatment. (2.5, 5.5, 6.3, 6.4, 8.8)
- Nephrolithiasis has been reported. Consider temporary interruption or discontinuation. (5.6, 6.4)
- Patients receiving REYATAZ may develop new onset or exacerbations of diabetes mellitus/hyperglycemia (5.7, 6.4), immune reconstitution syndrome (5.8), and redistribution/accumulation of body fat. (5.9)
- Hemophilia: Spontaneous bleeding may occur and additional factor VIII may be required. (5.10)

6 ADVERSE REACTIONS

Most common adverse reactions (≥2%) are nausea, jaundice/scleral icterus, rash, headache, abdominal pain, vomiting, insomnia, peripheral neurologic symptoms, dizziness, myalgia, diarrhea, depression, and fever. (6.1, 6.2)

To report SUSPECTED ADVERSE REACTIONS, contact Bristol-Myers Squibb at 1-800-721-5072 or FDA at 1-800-FDA-1088 or www.fda.gov/medwatch

7 DRUG INTERACTIONS

Coadministration of REYATAZ can alter the concentration of other drugs and other drugs may alter the concentration of atazanavir. The potential drug-drug interactions must be considered prior to and during therapy. (4, 5.1, 7, 12.3)

8 USE IN SPECIFIC POPULATIONS

- Pregnancy: Use only if the potential benefit justifies the potential risk. Physicians are encouraged to register patients in the Antiretroviral Pregnancy Registry. (8.1)
- Nursing mothers should be instructed not to breast-feed due to the potential for postnatal HIV transmission. (8.3)
- Hepatitis B or C co-infection: Monitor liver enzymes. (5.5, 6.3)
- Renal impairment: Do not use in treatment-experienced patients with end stage renal disease managed with hemodialysis. (2.4, 8.7)
- Hepatic impairment: REYATAZ should be used with caution in patients with mild to moderate hepatic impairment. Do not use REYATAZ in patients with severe hepatic impairment. REYATAZ/ritonavir is not recommended. (2.5, 8.8)

FULL PRESCRIBING INFORMATION

1 INDICATIONS AND USAGE

REYATAZ® (atazanavir sulfate) is indicated in combination with other antiretroviral agents for the treatment of HIV-1 infection. This indication is based on analyses of plasma HIV-1 RNA levels and CD4+ cell counts from controlled studies of 96 weeks duration in antiretroviral-naive and 48 weeks duration in antiretroviral-treatment-experienced adult and pediatric patients at least 6 years of age.

The following points should be considered when initiating therapy with REYATAZ:

- In Study AI424-045, REYATAZ/ritonavir and lopinavir/ritonavir were similar for the primary efficacy outcome measure of time-averaged difference in change from baseline in HIV RNA level. This study was not large enough to reach a definitive conclusion that REYATAZ/ritonavir and lopinavir/ritonavir are equivalent on the secondary efficacy outcome measure of proportions below the HIV RNA lower limit of detection [see Clinical Studies (14.2)].
- The number of baseline primary protease inhibitor mutations affects the virologic response to REYATAZ/ritonavir [see Clinical Pharmacology (12.4)].

2 DOSAGE AND ADMINISTRATION

General Dosing Recommendations:

- REYATAZ Capsules must be taken with food.
- Do not open the capsules.
- The recommended oral dosage of REYATAZ depends on the treatment history of the patient and the use of other coadministered drugs. When coadministered with H2-receptor antagonists or proton-pump inhibitors, dose separation may be required [see Dosage and Administration (2.1)].
- When coadministered with didanosine buffered or enteric-coated formulations, REYATAZ should be given (with food) 2 hours before or 1 hour after didanosine.
- REYATAZ without ritonavir is not recommended for treatment-experienced adult or pediatric patients with prior virologic failure [see Clinical Studies (14)].
- Efficacy and safety of REYATAZ with ritonavir in doses greater than 100 mg once daily have not been established. The use of higher ritonavir doses might alter the safety profile of atazanavir (cardiac effects, hyperbilirubinemia) and, therefore, is not recommended. Prescribers should consult the complete prescribing information for NORVIR® (ritonavir) when using this agent.

2.1 Recommended Adult Dosage

Table 1 summarizes the recommended REYATAZ dosing regimen in adults. All REYATAZ dosing regimens are to be administered as a single dose with food.

Table 1: REYATAZ Dosing Regimens
Treatment-Naive Patients | REYATAZ 300 mg with ritonavir 100 mg once daily
If unable to tolerate ritonavir | REYATAZ 400 mg once daily
When combined with any of the following: Tenofovir H2-receptor antagonist Proton-pump inhibitor | REYATAZ 300 mg with ritonavir 100 mg once daily
• The H2-receptor antagonist dose should not exceed a dose comparable to famotidine 40 mg twice daily.
Administer REYATAZ and ritonavir simultaneously with, and/or at least 10 hours after the H2-receptor
antagonist.
• If unable to tolerate ritonavir, administer REYATAZ 400 mg once daily at least 2 hours before and at least
10 hours after the H2-receptor antagonist. No single dose of the H2-receptor antagonist should exceed a dose
comparable to famotidine 20 mg and the total daily dose should not exceed a dose comparable to famotidine
40 mg.
• The proton-pump inhibitor dose should not exceed a dose comparable to omeprazole 20 mg daily and must
be taken approximately 12 hours prior to REYATAZ and ritonavir.
When combined with efavirenz | REYATAZ 400 mg with ritonavir 100 mg once daily
• Efavirenz should be administered on an empty stomach, preferably at bedtime.
Treatment-Experienced Patients | REYATAZ 300 mg with ritonavir 100 mg once daily
Do not coadminister with proton-pump inhibitors or efavirenz in treatment-experienced patients.
When given with an H2-receptor antagonist | REYATAZ 300 mg with ritonavir 100 mg once daily
• The H2-receptor antagonist dose should not exceed a dose comparable to famotidine 20 mg twice daily.
Administer REYATAZ and ritonavir simultaneously with, and/or at least 10 hours after the H2-receptor
antagonist.
When given with both tenofovirand an H2-receptor antagonist | REYATAZ 400 mg with ritonavir 100 mg once daily
• The H2-receptor antagonist dose should not exceed a dose comparable to famotidine 20 mg twice daily.
Administer REYATAZ and ritonavir simultaneously with, and/or at least 10 hours after the H2-receptor
antagonist.

[For these drugs and other antiretroviral agents for which dosing modification may be appropriate, see Drug Interactions (7).]

2.2 Recommended Pediatric Dosage

The recommended daily dosage of REYATAZ for pediatric patients (6 to less than 18 years of age) is based on body weight and should not exceed the recommended adult dosage. REYATAZ Capsules must be taken with food. The data are insufficient to recommend dosing of REYATAZ for any of the following: (1) patients less than 6 years of age, (2) without ritonavir in any pediatric patient less than 13 years of age, and (3) patients less than 40 kg receiving concomitant tenofovir, H2-receptor antagonists, or proton-pump inhibitors.

The recommended dosage of REYATAZ with ritonavir in pediatric patients at least 6 years of age is shown in Table 2.

Table 2: Dosage for Pediatric Patients (6 to less than 18 years of age) for REYATAZ Capsules with ritonavira
Body Weight | REYATAZ dose | ritonavir dose
15 kg to less than 20 kg | 150 mg | 100 mg
20 kg to less than 40 kg | 200 mg | 100 mg
at least 40 kg | 300 mg | 100 mg
a The REYATAZ and ritonavir dose should be taken once daily with food.

For treatment-naive patients at least 13 years of age and at least 40 kg, who are unable to tolerate ritonavir, the recommended dose is REYATAZ 400 mg (without ritonavir) once daily with food. For patients at least 13 years of age and at least 40 kg receiving concomitant tenofovir, H2-receptor antagonists, or proton-pump inhibitors, REYATAZ should not be administered without ritonavir.

2.3 Pregnancy

Dosing During Pregnancy and the Postpartum Period:

- REYATAZ should not be administered without ritonavir.
- REYATAZ should only be administered to pregnant women with HIV-1 strains susceptible to atazanavir.
- For pregnant patients, no dose adjustment is required for REYATAZ with the following exceptions:
  - For treatment-experienced pregnant women during the second or third trimester, when REYATAZ is
    coadministered with either an H2-receptor antagonist or tenofovir, REYATAZ 400 mg with ritonavir
    100 mg once daily is recommended. There are insufficient data to recommend a REYATAZ dose
    for use with both an H2-receptor antagonist and tenofovir in treatment-experienced pregnant
    women.
- No dose adjustment is required for postpartum patients. However, patients should be closely monitored for
  adverse events because atazanavir exposures could be higher during the first 2 months after delivery. [See
  Use in Specific Populations (8.1) and Clinical Pharmacology (12.3).]

2.4 Renal Impairment

For patients with renal impairment, including those with severe renal impairment who are not managed with hemodialysis, no dose adjustment is required for REYATAZ. Treatment-naive patients with end stage renal disease managed with hemodialysis should receive REYATAZ 300 mg with ritonavir 100 mg. REYATAZ should not be administered to HIV-treatment-experienced patients with end stage renal disease managed with hemodialysis. [See Use in Specific Populations (8.7).]

2.5 Hepatic Impairment

REYATAZ should be used with caution in patients with mild-to-moderate hepatic impairment. For patients with moderate hepatic impairment (Child-Pugh Class B) who have not experienced prior virologic failure, a dose reduction to 300 mg once daily should be considered. REYATAZ should not be used in patients with severe hepatic impairment (Child-Pugh Class C). REYATAZ/ritonavir has not been studied in subjects with hepatic impairment and is not recommended. [See Warnings and Precautions (5.5) and Use in Specific Populations (8.8).]

3 DOSAGE FORMS AND STRENGTHS

- 100 mg capsule with blue cap and white body, printed with white ink “BMS 100 mg” on the cap and with blue ink “3623” on the body.
- 150 mg capsule with blue cap and powder blue body, printed with white ink “BMS 150 mg” on the cap and with blue ink “3624” on the body.
- 200 mg capsule with blue cap and blue body, printed with white ink “BMS 200 mg” on the cap and with white ink “3631” on the body.
- 300 mg capsule with red cap and blue body, printed with white ink “BMS 300 mg” on the cap and with white ink “3622” on the body.

4 CONTRAINDICATIONS

REYATAZ (atazanavir sulfate) is contraindicated:

- in patients with previously demonstrated clinically significant hypersensitivity (eg, Stevens-Johnson syndrome, erythema multiforme, or toxic skin eruptions) to any of the components of this product.
- when coadministered with drugs that are highly dependent on CYP3A or UGT1A1 for clearance, and for which elevated plasma concentrations are associated with serious and/or life-threatening events. These and other contraindicated drugs are listed in Table 3.

Table 3: Drugs That Are Contraindicated with REYATAZ (atazanavir) (Information in the table applies to REYATAZ with or without ritonavir, unless otherwise indicated)
Drug Class | Drugs within class that are contraindicated with REYATAZ | Clinical Comment
Alpha 1-Adrenoreceptor Antagonist | Alfuzosin | Potential for increased alfuzosin concentrations, which can result in hypotension.
Antimycobacterials | Rifampin | Rifampin substantially decreases plasma concentrations of atazanavir, which may result in loss of therapeutic effect and development of resistance.
Antineoplastics | Irinotecan | Atazanavir inhibits UGT1A1 and may interfere with the metabolism of irinotecan, resulting in increased irinotecan toxicities.
Benzodiazepines | Triazolam, orally administered midazolama | Triazolam and orally administered midazolam are extensively metabolized by CYP3A4. Coadministration of triazolam or orally administered midazolam with REYATAZ may cause large increases in the concentration of these benzodiazepines. Potential for serious and/or life-threatening events such as prolonged or increased sedation or respiratory depression.
Ergot Derivatives | Dihydroergotamine, ergotamine, ergonovine, methylergonovine | Potential for serious and/or life-threatening events such as acute ergot toxicity characterized by peripheral vasospasm and ischemia of the extremities and other tissues.
GI Motility Agent | Cisapride | Potential for serious and/or life-threatening reactions such as cardiac arrhythmias.
Herbal Products | St. John’s wort (Hypericum perforatum) | Patients taking REYATAZ should not use products containing St. John’s wort because coadministration may be expected to reduce plasma concentrations of atazanavir. This may result in loss of therapeutic effect and development of resistance.
HMG-CoA Reductase Inhibitors | Lovastatin, simvastatin | Potential for serious reactions such as myopathy including rhabdomyolysis.
Neuroleptic | Pimozide | Potential for serious and/or life-threatening reactions such as cardiac arrhythmias.
PDE5 Inhibitor | Sildenafilb when dosed as REVATIO® for the treatment of pulmonary arterial hypertension | A safe and effective dose in combination with REYATAZ has not been established for sildenafil (REVATIO®) when used for the treatment of pulmonary hypertension. There is increased potential for sildenafil-associated adverse events (which include visual disturbances, hypotension, priapism, and syncope).
Protease Inhibitors | Indinavir | Both REYATAZ and indinavir are associated with indirect (unconjugated) hyperbilirubinemia.
a See Drug Interactions, Table 13 (7) for parenterally administered midazolam.
b See Drug Interactions, Table 13 (7) for sildenafil when dosed as VIAGRA® for erectile dysfunction.

5 WARNINGS AND PRECAUTIONS

5.1 Drug Interactions

See Table 3 for a listing of drugs that are contraindicated for use with REYATAZ due to potentially life-threatening adverse events, significant drug interactions, or loss of virologic activity. [See Contraindications (4).] Please refer to Table 13 for established and other potentially significant drug interactions [see Drug Interactions (7.3)].

5.2 Cardiac Conduction Abnormalities

Atazanavir has been shown to prolong the PR interval of the electrocardiogram in some patients. In healthy volunteers and in patients, abnormalities in atrioventricular (AV) conduction were asymptomatic and generally limited to first-degree AV block. There have been reports of second-degree AV block and other conduction abnormalities [see Adverse Reactions (6.4) and Overdosage (10)]. In clinical trials that included electrocardiograms, asymptomatic first-degree AV block was observed in 5.9% of atazanavir-treated patients (n=920), 5.2% of lopinavir/ritonavir-treated patients (n=252), 10.4% of nelfinavir-treated patients (n=48), and 3.0% of efavirenz-treated patients (n=329). In Study AI424-045, asymptomatic first-degree AV block was observed in 5% (6/118) of atazanavir/ritonavir-treated patients and 5% (6/116) of lopinavir/ritonavir-treated patients who had on-study electrocardiogram measurements. Because of limited clinical experience in patients with preexisting conduction system disease (eg, marked first-degree AV block or second- or third-degree AV block), atazanavir should be used with caution in these patients. [See Clinical Pharmacology (12.2).]

Atazanavir in combination with diltiazem increased diltiazem plasma concentration by 2-fold with an additive effect on the PR interval. When used in combination with atazanavir, a dose reduction of diltiazem by one-half should be considered and ECG monitoring is recommended. In a pharmacokinetic study between atazanavir 400 mg once daily and atenolol 50 mg once daily, no clinically significant additive effect of atazanavir and atenolol on the PR interval was observed. Dose adjustment of atenolol is not required when used in combination with atazanavir. [See Drug Interactions (7) and Clinical Pharmacology (12.2).] Pharmacokinetic studies between atazanavir and other drugs that prolong the PR interval including beta blockers [other than atenolol, see Drug Interactions (7)], verapamil, and digoxin have not been performed. An additive effect of atazanavir and these drugs cannot be excluded; therefore, caution should be exercised when atazanavir is given concurrently with these drugs, especially those that are metabolized by CYP3A (eg, verapamil).

5.3 Rash

In controlled clinical trials, rash (all grades, regardless of causality) occurred in approximately 20% of patients treated with REYATAZ. The median time to onset of rash in clinical studies was 7.3 weeks and the median duration of rash was 1.4 weeks. Rashes were generally mild-to-moderate maculopapular skin eruptions. Treatment-emergent adverse reactions of moderate or severe rash (occurring at a rate of ≥2%) are presented for the individual clinical studies [see Adverse Reactions (6.1)]. Dosing with REYATAZ was often continued without interruption in patients who developed rash. The discontinuation rate for rash in clinical trials was <1%. REYATAZ should be discontinued if severe rash develops. Cases of Stevens-Johnson syndrome, erythema multiforme, and toxic skin eruptions have been reported in patients receiving REYATAZ. [See Contraindications (4).]

5.4 Hyperbilirubinemia

Most patients taking REYATAZ experience asymptomatic elevations in indirect (unconjugated) bilirubin related to inhibition of UDP-glucuronosyl transferase (UGT). This hyperbilirubinemia is reversible upon discontinuation of REYATAZ. Hepatic transaminase elevations that occur with hyperbilirubinemia should be evaluated for alternative etiologies. No long-term safety data are available for patients experiencing persistent elevations in total bilirubin >5 times ULN. Alternative antiretroviral therapy to REYATAZ may be considered if jaundice or scleral icterus associated with bilirubin elevations presents cosmetic concerns for patients. Dose reduction of atazanavir is not recommended since long-term efficacy of reduced doses has not been established. [See Adverse Reactions (6.1, 6.2).]

5.5 Hepatotoxicity

Caution should be exercised when administering REYATAZ to patients with hepatic impairment because atazanavir concentrations may be increased. [See Dosage and Administration (2.5).] Patients with underlying hepatitis B or C viral infections or marked elevations in transaminases before treatment may be at increased risk for developing further transaminase elevations or hepatic decompensation. In these patients, hepatic laboratory testing should be conducted prior to initiating therapy with REYATAZ and during treatment. [See Adverse Reactions (6.3) and Use in Specific Populations (8.8).]

5.6 Nephrolithiasis

Cases of nephrolithiasis were reported during postmarketing surveillance in HIV-infected patients receiving REYATAZ therapy. Because these events were reported voluntarily during clinical practice, estimates of frequency cannot be made. If signs or symptoms of nephrolithiasis occur, temporary interruption or discontinuation of therapy may be considered. [See Adverse Reactions (6.4).]

5.7 Diabetes Mellitus/Hyperglycemia

New-onset diabetes mellitus, exacerbation of preexisting diabetes mellitus, and hyperglycemia have been reported during postmarketing surveillance in HIV-infected patients receiving protease inhibitor therapy. Some patients required either initiation or dose adjustments of insulin or oral hypoglycemic agents for treatment of these events. In some cases, diabetic ketoacidosis has occurred. In those patients who discontinued protease inhibitor therapy, hyperglycemia persisted in some cases. Because these events have been reported voluntarily during clinical practice, estimates of frequency cannot be made and a causal relationship between protease inhibitor therapy and these events has not been established. [See Adverse Reactions (6.4).]

5.8 Immune Reconstitution Syndrome

Immune reconstitution syndrome has been reported in patients treated with combination antiretroviral therapy, including REYATAZ. During the initial phase of combination antiretroviral treatment, patients whose immune system responds may develop an inflammatory response to indolent or residual opportunistic infections (such as Mycobacterium avium infection, cytomegalovirus, Pneumocystis jiroveci pneumonia, or tuberculosis), which may necessitate further evaluation and treatment.

5.9 Fat Redistribution

Redistribution/accumulation of body fat including central obesity, dorsocervical fat enlargement (buffalo hump), peripheral wasting, facial wasting, breast enlargement, and “cushingoid appearance” have been observed in patients receiving antiretroviral therapy. The mechanism and long-term consequences of these events are currently unknown. A causal relationship has not been established.

5.10 Hemophilia

There have been reports of increased bleeding, including spontaneous skin hematomas and hemarthrosis, in patients with hemophilia type A and B treated with protease inhibitors. In some patients additional factor VIII was given. In more than half of the reported cases, treatment with protease inhibitors was continued or reintroduced. A causal relationship between protease inhibitor therapy and these events has not been established.

5.11 Resistance/Cross-Resistance

Various degrees of cross-resistance among protease inhibitors have been observed. Resistance to atazanavir may not preclude the subsequent use of other protease inhibitors. [See Clinical Pharmacology (12.4).]

6 ADVERSE REACTIONS

The following adverse reactions are discussed in greater detail in other sections of the labeling:

- cardiac conduction abnormalities [see Warnings and Precautions (5.2)]
- rash [see Warnings and Precautions (5.3)]
- hyperbilirubinemia [see Warnings and Precautions (5.4)]
- nephrolithiasis [see Warnings and Precautions (5.6)]

Because clinical trials are conducted under widely varying conditions, adverse reaction rates observed in the clinical trials of a drug cannot be directly compared to rates in the clinical trials of another drug and may not reflect the rates observed in practice.

6.1 Clinical Trial Experience in Adults

Treatment-Emergent Adverse Reactions in Treatment-Naive Patients

The safety profile of REYATAZ in treatment-naive adults is based on 1625 HIV-1 infected patients in clinical trials. 536 patients received REYATAZ 300 mg with ritonavir 100 mg and 1089 patients received REYATAZ 400 mg or higher (without ritonavir).

The most common adverse reactions are nausea, jaundice/scleral icterus, and rash.

Selected clinical adverse reactions of moderate or severe intensity reported in ≥2% of treatment-naive patients receiving combination therapy including REYATAZ 300 mg with ritonavir 100 mg and REYATAZ 400 mg (without ritonavir) are presented in Tables 4 and 5, respectively.

Table 4: Selected Treatment-Emergent Adverse Reactionsa of Moderate or Severe Intensity Reported in ≥2% of Adult Treatment-Naive Patients,b Study AI424-138
 | 96 weeksc | 96 weeksc
 | REYATAZ 300 mg with ritonavir 100 mg (once daily) and tenofovir with emtricitabined | lopinavir 400 mg with ritonavir 100 mg (twice daily) and tenofovir with emtricitabined
 | (n=441) | (n=437)
Digestive System
Nausea | 4% | 8%
Jaundice/scleral icterus | 5% | *
Diarrhea | 2% | 12%
Skin and Appendages
Rash | 3% | 2%
* None reported in this treatment arm.
a Includes events of possible, probable, certain, or unknown relationship to treatment regimen.
b Based on the regimen containing REYATAZ.
c Median time on therapy.
d As a fixed-dose combination: 300 mg tenofovir, 200 mg emtricitabine once daily.

Table 5: Selected Treatment-Emergent Adverse Reactionsa of Moderate or Severe Intensity Reported in ≥2% of Adult Treatment-Naive Patients,b Studies AI424-034, AI424-007, and AI424-008
 | Study AI424-034 |  | Studies AI424-007, -008
 | 64 weeksc REYATAZ 400 mg once daily + lamivudine + zidovudinee | 64 weeksc efavirenz 600 mg once daily + lamivudine + zidovudinee | 120 weeksc,d REYATAZ 400 mg once daily + stavudine + lamivudine or didanosine | 73 weeksc,d nelfinavir 750 mg TID or 1250 mg BID + stavudine + lamivudine or didanosine
 | (n=404) | (n=401) | (n=279) | (n=191)
Body as a Whole
Headache | 6% | 6% | 1% | 2%
Digestive System
Nausea | 14% | 12% | 6% | 4%
Jaundice/scleral icterus | 7% | * | 7% | *
Vomiting | 4% | 7% | 3% | 3%
Abdominal pain | 4% | 4% | 4% | 2%
Diarrhea | 1% | 2% | 3% | 16%
Nervous System
Insomnia | 3% | 3% | <1% | *
Dizziness | 2% | 7% | <1% | *
Peripheral neurologic symptoms | <1% | 1% | 4% | 3%
Skin and Appendages
Rash | 7% | 10% | 5% | 1%
* None reported in this treatment arm.
a Includes events of possible, probable, certain, or unknown relationship to treatment regimen.
b Based on regimens containing REYATAZ.
c Median time on therapy.
d Includes long-term follow-up.
e As a fixed-dose combination: 150 mg lamivudine, 300 mg zidovudine twice daily.

Treatment-Emergent Adverse Reactions in Treatment-Experienced Patients

The safety profile of REYATAZ in treatment-experienced adults is based on 119 HIV-1 infected patients in clinical trials.

The most common adverse reactions are jaundice/scleral icterus and myalgia.

Selected clinical adverse reactions of moderate or severe intensity reported in ≥2% of treatment-experienced patients receiving REYATAZ/ritonavir are presented in Table 6.

Table 6: Selected Treatment-Emergent Adverse Reactionsa of Moderate or Severe Intensity Reported in ≥2% of Adult Treatment-Experienced Patients,b Study AI424-045
 | 48 weeksc REYATAZ/ritonavir 300/100 mg once daily + tenofovir + NRTI | 48 weeksc lopinavir/ritonavir 400/100 mg twice dailyd + tenofovir + NRTI
 | (n=119) | (n=118)
Body as a Whole
Fever | 2% | *
Digestive System
Jaundice/scleral icterus | 9% | *
Diarrhea | 3% | 11%
Nausea | 3% | 2%
Nervous System
Depression | 2% | <1%
Musculoskeletal System
Myalgia | 4% | *
* None reported in this treatment arm.
a Includes events of possible, probable, certain, or unknown relationship to treatment regimen.
b Based on the regimen containing REYATAZ.
c Median time on therapy.
d As a fixed-dose combination.

Laboratory Abnormalities in Treatment-Naive Patients

The percentages of adult treatment-naive patients treated with combination therapy including REYATAZ (atazanavir sulfate) 300 mg with ritonavir 100 mg and REYATAZ 400 mg (without ritonavir) with Grade 3–4 laboratory abnormalities are presented in Tables 7 and 8, respectively.

Table 7: Grade 3–4 Laboratory Abnormalities Reported in ≥2% of Adult Treatment-Naive Patients,a Study AI424-138
Variable | Limitc | 96 weeksb | 96 weeksb
Variable | Limitc | REYATAZ 300 mg with ritonavir 100 mg (once daily) and tenofovir with emtricitabined | lopinavir 400 mg with ritonavir 100 mg (twice daily) and tenofovir with emtricitabined
Variable | Limitc | (n=441) | (n=437)
Chemistry | High
SGOT/AST | ≥5.1 x ULN | 3% | 1%
SGPT/ALT | ≥5.1 x ULN | 3% | 2%
Total Bilirubin | ≥2.6 x ULN | 44% | <1%
Lipase | ≥2.1 x ULN | 2% | 2%
Creatine Kinase | ≥5.1 x ULN | 8% | 7%
Total Cholesterol | ≥240 mg/dL | 11% | 25%
Hematology | Low
Neutrophils | <750 cells/mm^3 | 5% | 2%
a Based on the regimen containing REYATAZ.
b Median time on therapy.
c ULN = upper limit of normal.
d As a fixed-dose combination: 300 mg tenofovir, 200 mg emtricitabine once daily.

Table 8: Grade 3–4 Laboratory Abnormalities Reported in ≥2% of Adult Treatment-Naive Patients,a Studies AI424-034, AI424-007, and AI424-008
Variable | Limitd | Study AI424-034 |  | Studies AI424-007, -008
Variable | Limitd | 64 weeksb | 64 weeksb | 120 weeksb,c | 73 weeksb,c
Variable | Limitd | REYATAZ 400 mg once daily + lamivudine + zidovudinee | efavirenz 600 mg once daily + lamivudine + zidovudinee | REYATAZ 400 mg once daily + stavudine + lamivudine or + stavudine + didanosine | nelfinavir 750 mg TID or 1250 mg BID + stavudine + lamivudine or + stavudine + didanosine
Variable | Limitd | (n=404) | (n=401) | (n=279) | (n=191)
Chemistry | High
SGOT/AST | ≥5.1 x ULN | 2% | 2% | 7% | 5%
SGPT/ALT | ≥5.1 x ULN | 4% | 3% | 9% | 7%
Total Bilirubin | ≥2.6 x ULN | 35% | <1% | 47% | 3%
Amylase | ≥2.1 x ULN | * | * | 14% | 10%
Lipase | ≥2.1 x ULN | <1% | 1% | 4% | 5%
Creatine Kinase | ≥5.1 x ULN | 6% | 6% | 11% | 9%
Total Cholesterol | ≥240 mg/dL | 6% | 24% | 19% | 48%
Triglycerides | ≥751 mg/dL | <1% | 3% | 4% | 2%
Hematology | Low
Hemoglobin | <8.0 g/dL | 5% | 3% | <1% | 4%
Neutrophils | <750 cells/mm^3 | 7% | 9% | 3% | 7%
* None reported in this treatment arm.
a Based on regimen(s) containing REYATAZ.
b Median time on therapy.
c Includes long-term follow-up.
d ULN = upper limit of normal.
e As a fixed-dose combination: 150 mg lamivudine, 300 mg zidovudine twice daily.

Laboratory Abnormalities in Treatment-Experienced Patients

The percentages of adult treatment-experienced patients treated with combination therapy including REYATAZ/ritonavir with Grade 3–4 laboratory abnormalities are presented in Table 9.

Table 9: Grade 3–4 Laboratory Abnormalities Reported in ≥2% of Adult Treatment-Experienced Patients, Study AI424-045a
Variable | Limitc | 48 weeksb | 48 weeksb
Variable | Limitc | REYATAZ/ritonavir 300/100 mg once daily + tenofovir + NRTI | lopinavir/ritonavir 400/100 mg twice dailyd + tenofovir + NRTI
Variable | Limitc | (n=119) | (n=118)
Chemistry | High
SGOT/AST | ≥5.1 x ULN | 3% | 3%
SGPT/ALT | ≥5.1 x ULN | 4% | 3%
Total Bilirubin | ≥2.6 x ULN | 49% | <1%
Lipase | ≥2.1 x ULN | 5% | 6%
Creatine Kinase | ≥5.1 x ULN | 8% | 8%
Total Cholesterol | ≥240 mg/dL | 25% | 26%
Triglycerides | ≥751 mg/dL | 8% | 12%
Glucose | ≥251 mg/dL | 5% | <1%
Hematology | Low
Platelets | <50,000 cells/mm^3 | 2% | 3%
Neutrophils | <750 cells/mm^3 | 7% | 8%
a Based on regimen(s) containing REYATAZ.
b Median time on therapy.
c ULN = upper limit of normal.
d As a fixed-dose combination.

Lipids, Change from Baseline in Treatment-Naive Patients

For Study AI424-138 and Study AI424-034, changes from baseline in LDL-cholesterol, HDL-cholesterol, total cholesterol, and triglycerides are shown in Tables 10 and 11, respectively.

Table 10: Lipid Values, Mean Change from Baseline, Study AI424-138
 | REYATAZ/ritonavira,b |  |  |  |  | lopinavir/ritonavirb,c
 | Baseline | Week 48 |  | Week 96 |  | Baseline | Week 48 |  | Week 96
 | mg/dL | mg/dL | Changed | mg/dL | Changed | mg/dL | mg/dL | Changed | mg/dL | Changed
 | (n=428e) | (n=372e) | (n=372e) | (n=342e) | (n=342e) | (n=424e) | (n=335e) | (n=335e) | (n=291e) | (n=291e)
 | LDL-Cholesterolf | 92 | 105 | +14% | 105 | +14% | 93 | 111 | +19% | 110 | +17%
HDL-Cholesterolf | 37 | 46 | +29% | 44 | +21% | 36 | 48 | +37% | 46 | +29%
Total Cholesterolf | 149 | 169 | +13% | 169 | +13% | 150 | 187 | +25% | 186 | +25%
Triglyceridesf | 126 | 145 | +15% | 140 | +13% | 129 | 194 | +52% | 184 | +50%
a REYATAZ 300 mg with ritonavir 100 mg once daily with the fixed-dose combination: 300 mg tenofovir, 200 mg emtricitabine once daily.
b Values obtained after initiation of serum lipid-reducing agents were not included in these analyses. At baseline, serum lipid-reducing agents were used in 1% in the lopinavir/ritonavir treatment arm and 1% in the REYATAZ/ritonavir arm. Through Week 48, serum lipid-reducing agents were used in 8% in the lopinavir/ritonavir treatment arm and 2% in the REYATAZ/ritonavir arm. Through Week 96, serum lipid-reducing agents were used in 10% in the lopinavir/ritonavir treatment arm and 3% in the REYATAZ/ritonavir arm.
c Lopinavir 400 mg with ritonavir 100 mg twice daily with the fixed-dose combination 300 mg tenofovir, 200 mg emtricitabine once daily.
d The change from baseline is the mean of within-patient changes from baseline for patients with both baseline and Week 48 or Week 96 values and is not a simple difference of the baseline and Week 48 or Week 96 mean values, respectively.
e Number of patients with LDL-cholesterol measured.
f Fasting.

Table 11: Lipid Values, Mean Change from Baseline, Study AI424-034
 | REYATAZa,b |  |  | efavirenzb,c
 | Baseline | Week 48 | Week 48 | Baseline | Week 48 | Week 48
 | mg/dL | mg/dL | Changed | mg/dL | mg/dL | Changed
 | (n=383e) | (n=283e) | (n=272e) | (n=378e) | (n=264e) | (n=253e)
LDL-Cholesterolf | 98 | 98 | +1% | 98 | 114 | +18%
HDL-Cholesterol | 39 | 43 | +13% | 38 | 46 | +24%
Total Cholesterol | 164 | 168 | +2% | 162 | 195 | +21%
Triglyceridesf | 138 | 124 | -9% | 129 | 168 | +23%
a REYATAZ 400 mg once daily with the fixed-dose combination: 150 mg lamivudine, 300 mg zidovudine twice daily.
b Values obtained after initiation of serum lipid-reducing agents were not included in these analyses. At baseline, serum lipid-reducing agents were used in 0% in the efavirenz treatment arm and <1% in the REYATAZ arm. Through Week 48, serum lipid-reducing agents were used in 3% in the efavirenz treatment arm and 1% in the REYATAZ arm.
c Efavirenz 600 mg once daily with the fixed-dose combination: 150 mg lamivudine, 300 mg zidovudine twice daily.
d The change from baseline is the mean of within-patient changes from baseline for patients with both baseline and Week 48 values and is not a simple difference of the baseline and Week 48 mean values.
e Number of patients with LDL-cholesterol measured.
f Fasting.

Lipids, Change from Baseline in Treatment-Experienced Patients

For Study AI424-045, changes from baseline in LDL-cholesterol, HDL-cholesterol, total cholesterol, and triglycerides are shown in Table 12. The observed magnitude of dyslipidemia was less with REYATAZ/ritonavir than with lopinavir/ritonavir. However, the clinical impact of such findings has not been demonstrated.

Table 12: Lipid Values, Mean Change from Baseline, Study AI424-045
 | REYATAZ/ritonavira,b |  |  | lopinavir/ritonavirb,c
 | Baseline | Week 48 | Week 48 | Baseline | Week 48 | Week 48
 | mg/dL | mg/dL | Changed | mg/dL | mg/dL | Changed
 | (n=111e) | (n=75e) | (n=74e) | (n=108e) | (n=76e) | (n=73e)
LDL-Cholesterolf | 108 | 98 | -10% | 104 | 103 | +1%
HDL-Cholesterol | 40 | 39 | -7% | 39 | 41 | +2%
Total Cholesterol | 188 | 170 | -8% | 181 | 187 | +6%
Triglyceridesf | 215 | 161 | -4% | 196 | 224 | +30%
a REYATAZ 300 mg once daily + ritonavir + tenofovir + 1 NRTI.
b Values obtained after initiation of serum lipid-reducing agents were not included in these analyses. At baseline, serum lipid-reducing agents were used in 4% in the lopinavir/ritonavir treatment arm and 4% in the REYATAZ/ritonavir arm. Through Week 48, serum lipid-reducing agents were used in 19% in the lopinavir/ritonavir treatment arm and 8% in the REYATAZ/ritonavir arm.
c Lopinavir/ritonavir (400/100 mg) BID + tenofovir + 1 NRTI.
d The change from baseline is the mean of within-patient changes from baseline for patients with both baseline and Week 48 values and is not a simple difference of the baseline and Week 48 mean values.
e Number of patients with LDL-cholesterol measured.
f Fasting.

6.2 Clinical Trial Experience in Pediatric Patients

The safety and tolerability of REYATAZ Capsules with and without ritonavir have been established in pediatric patients at least 6 years of age from the open-label, multicenter clinical trial PACTG 1020A. Use of REYATAZ in pediatric patients less than 6 years of age is under investigation.

The safety profile of REYATAZ in pediatric patients (6 to less than 18 years of age) was generally similar to that observed in clinical studies of REYATAZ in adults. The most common Grade 2–4 adverse events (≥5%, regardless of causality) reported in pediatric patients were cough (21%), fever (18%), jaundice/scleral icterus (15%), rash (14%), vomiting (12%), diarrhea (9%), headache (8%), peripheral edema (7%), extremity pain (6%), nasal congestion (6%), oropharyngeal pain (6%), wheezing (6%), and rhinorrhea (6%). Asymptomatic second-degree atrioventricular block was reported in <2% of patients. The most common Grade 3–4 laboratory abnormalities occurring in pediatric patients were elevation of total bilirubin (≥3.2 mg/dL, 58%), neutropenia (9%), and hypoglycemia (4%). All other Grade 3–4 laboratory abnormalities occurred with a frequency of less than 3%.

6.3 Patients Co-infected With Hepatitis B and/or Hepatitis C Virus

Liver function tests should be monitored in patients with a history of hepatitis B or C.

In study AI424-138, 60 patients treated with REYATAZ/ritonavir 300 mg/100 mg once daily, and 51 patients treated with lopinavir/ritonavir 400 mg/100 mg twice daily, each with fixed dose tenofovir-emtricitabine, were seropositive for hepatitis B and/or C at study entry. ALT levels >5 times ULN developed in 10% (6/60) of the REYATAZ/ritonavir-treated patients and 8% (4/50) of the lopinavir/ritonavir-treated patients. AST levels >5 times ULN developed in 10% (6/60) of the REYATAZ/ritonavir-treated patients and none (0/50) of the lopinavir/ritonavir-treated patients.

In study AI424-045, 20 patients treated with REYATAZ/ritonavir 300 mg/100 mg once daily, and 18 patients treated with lopinavir/ritonavir 400 mg/100 mg twice daily, were seropositive for hepatitis B and/or C at study entry. ALT levels >5 times ULN developed in 25% (5/20) of the REYATAZ/ritonavir-treated patients and 6% (1/18) of the lopinavir/ritonavir-treated patients. AST levels >5 times ULN developed in 10% (2/20) of the REYATAZ/ritonavir-treated patients and 6% (1/18) of the lopinavir/ritonavir-treated patients.

In studies AI424-008 and AI424-034, 74 patients treated with 400 mg of REYATAZ (atazanavir sulfate) once daily, 58 who received efavirenz, and 12 who received nelfinavir were seropositive for hepatitis B and/or C at study entry. ALT levels >5 times the upper limit of normal (ULN) developed in 15% of the REYATAZ-treated patients, 14% of the efavirenz-treated patients, and 17% of the nelfinavir-treated patients. AST levels >5 times ULN developed in 9% of the REYATAZ-treated patients, 5% of the efavirenz-treated patients, and 17% of the nelfinavir-treated patients. Within atazanavir and control regimens, no difference in frequency of bilirubin elevations was noted between seropositive and seronegative patients. [See Warnings and Precautions (5.5).]

6.4 Postmarketing Experience

The following events have been identified during postmarketing use of REYATAZ. Because these reactions are reported voluntarily from a population of unknown size, it is not always possible to reliably estimate their frequency or establish a causal relationship to drug exposure.

Body as a Whole: edema

Cardiovascular System: second-degree AV block, third-degree AV block, left bundle branch block, QTc prolongation [see Warnings and Precautions (5.2)]

Gastrointestinal System: pancreatitis

Hepatic System: hepatic function abnormalities

Hepatobiliary Disorders: cholelithiasis, cholecystitis, cholestasis

Metabolic System and Nutrition Disorders: diabetes mellitus, hyperglycemia [see Warnings and Precautions (5.7)]

Musculoskeletal System: arthralgia

Renal System: nephrolithiasis [see Warnings and Precautions (5.6)]

Skin and Appendages: alopecia, maculopapular rash [see Contraindications (4) and Warnings and Precautions (5.3)], pruritus

7 DRUG INTERACTIONS

See also Contraindications (4) and Clinical Pharmacology (12.3).

7.1 Potential for REYATAZ to Affect Other Drugs

Atazanavir is an inhibitor of CYP3A and UGT1A1. Coadministration of REYATAZ and drugs primarily metabolized by CYP3A or UGT1A1 may result in increased plasma concentrations of the other drug that could increase or prolong its therapeutic and adverse effects.

Atazanavir is a weak inhibitor of CYP2C8. Caution should be used when REYATAZ without ritonavir is coadministered with drugs highly dependent on CYP2C8 with narrow therapeutic indices (eg, paclitaxel, repaglinide). When REYATAZ with ritonavir is coadministered with substrates of CYP2C8, clinically significant interactions are not expected. [See Clinical Pharmacology, Table 14 (12.3).]

The magnitude of CYP3A-mediated drug interactions on coadministered drug may change when REYATAZ is coadministered with ritonavir. See the complete prescribing information for NORVIR® (ritonavir) for information on drug interactions with ritonavir.

7.2 Potential for Other Drugs to Affect Atazanavir

Atazanavir is a CYP3A4 substrate; therefore, drugs that induce CYP3A4 may decrease atazanavir plasma concentrations and reduce REYATAZ’s therapeutic effect.

Atazanavir solubility decreases as pH increases. Reduced plasma concentrations of atazanavir are expected if proton-pump inhibitors, antacids, buffered medications, or H2-receptor antagonists are administered with atazanavir.

7.3 Established and Other Potentially Significant Drug Interactions

Table 13 provides dosing recommendations as a result of drug interactions with REYATAZ. These recommendations are based on either drug interaction studies or predicted interactions due to the expected magnitude of interaction and potential for serious events or loss of efficacy.

Table 13: Established and Other Potentially Significant Drug Interactions: Alteration in Dose or Regimen May Be Recommended Based on Drug Interaction Studiesa or Predicted Interactions (Information in the table applies to REYATAZ with or without ritonavir, unless otherwise indicated)
Concomitant Drug Class: Specific Drugs | Effect on Concentration of Atazanavir or Concomitant Drug | Clinical Comment
HIV Antiviral Agents
Nucleoside Reverse Transcriptase Inhibitors (NRTIs): didanosine buffered formulations enteric-coated (EC) capsules | ↓ atazanavir ↓ didanosine | Coadministration of REYATAZ with didanosine buffered tablets resulted in a marked decrease in atazanavir exposure. It is recommended that REYATAZ be given (with food) 2 h before or 1 h after didanosine buffered formulations. Simultaneous administration of didanosine EC and REYATAZ with food results in a decrease in didanosine exposure. Thus, REYATAZ and didanosine EC should be administered at different times.
Nucleotide Reverse Transcriptase Inhibitors: tenofovir disoproxil fumarate | ↓ atazanavir ↑ tenofovir | Tenofovir may decrease the AUC and Cmin of atazanavir. When coadministered with tenofovir, it is recommended that REYATAZ 300 mg be given with ritonavir 100 mg and tenofovir 300 mg (all as a single daily dose with food). REYATAZ without ritonavir should not be coadministered with tenofovir. REYATAZ increases tenofovir concentrations. The mechanism of this interaction is unknown. Higher tenofovir concentrations could potentiate tenofovir-associated adverse events, including renal disorders. Patients receiving REYATAZ and tenofovir should be monitored for tenofovir-associated adverse events. For pregnant women taking REYATAZ with ritonavir and tenofovir, see Dosage and Administration (2.3).
Non-nucleoside Reverse Transcriptase Inhibitors (NNRTIs): efavirenz | ↓ atazanavir | Efavirenz decreases atazanavir exposure. In treatment-naive patients: If REYATAZ is combined with efavirenz, REYATAZ 400 mg (two 200-mg capsules) with ritonavir 100 mg should be administered once daily all as a single dose with food, and efavirenz 600 mg should be administered once daily on an empty stomach, preferably at bedtime. In treatment-experienced patients: Do not coadminister REYATAZ with efavirenz in treatment-experienced patients due to decreased atazanavir exposure.
Non-nucleoside Reverse Transcriptase Inhibitors: nevirapine | ↓ atazanavir ↑ nevirapine | Do not coadminister REYATAZ with nevirapine because:; - Nevirapine substantially decreases atazanavir exposure. - Potential risk for nevirapine associated toxicity due to increased nevirapine exposures.
Protease Inhibitors: saquinavir (soft gelatin capsules) | ↑ saquinavir | Appropriate dosing recommendations for this combination, with or without ritonavir, with respect to efficacy and safety have not been established. In a clinical study, saquinavir 1200 mg coadministered with REYATAZ 400 mg and tenofovir 300 mg (all given once daily) plus nucleoside analogue reverse transcriptase inhibitors did not provide adequate efficacy [see Clinical Studies (14.2)].
Protease Inhibitors: ritonavir | ↑ atazanavir | If REYATAZ is coadministered with ritonavir, it is recommended that REYATAZ 300 mg once daily be given with ritonavir 100 mg once daily with food. See the complete prescribing information for NORVIR® (ritonavir) for information on drug interactions with ritonavir.
Protease Inhibitors: others | ↑ other protease inhibitor | REYATAZ/ritonavir: Although not studied, the coadministration of REYATAZ/ritonavir and other protease inhibitors would be expected to increase exposure to the other protease inhibitor. Such coadministration is not recommended.
Other Agents
Antacids and buffered medications | ↓ atazanavir | Reduced plasma concentrations of atazanavir are expected if antacids, including buffered medications, are administered with REYATAZ. REYATAZ should be administered 2 hours before or 1 hour after these medications.
Antiarrhythmics: amiodarone, bepridil, lidocaine (systemic), quinidine | ↑ amiodarone, bepridil, lidocaine (systemic), quinidine | Coadministration with REYATAZ has the potential to produce serious and/or life-threatening adverse events and has not been studied. Caution is warranted and therapeutic concentration monitoring of these drugs is recommended if they are used concomitantly with REYATAZ (atazanavir sulfate).
Anticoagulants: warfarin | ↑ warfarin | Coadministration with REYATAZ has the potential to produce serious and/or life-threatening bleeding and has not been studied. It is recommended that INR (International Normalized Ratio) be monitored.
Antidepressants: tricyclic antidepressants | ↑ tricyclic antidepressants | Coadministration with REYATAZ has the potential to produce serious and/or life-threatening adverse events and has not been studied. Concentration monitoring of these drugs is recommended if they are used concomitantly with REYATAZ.
trazodone | ↑ trazodone | Concomitant use of trazodone and REYATAZ with or without ritonavir may increase plasma concentrations of trazodone. Adverse events of nausea, dizziness, hypotension, and syncope have been observed following coadministration of trazodone and ritonavir. If trazodone is used with a CYP3A4 inhibitor such as REYATAZ, the combination should be used with caution and a lower dose of trazodone should be considered.
Antifungals: ketoconazole, itraconazole | REYATAZ/ritonavir: ↑ ketoconazole ↑ itraconazole | Coadministration of ketoconazole has only been studied with REYATAZ without ritonavir (negligible increase in atazanavir AUC and Cmax). Due to the effect of ritonavir on ketoconazole, high doses of ketoconazole and itraconazole (>200 mg/day) should be used cautiously with REYATAZ/ritonavir.
Antifungals: voriconazole | Effect is unknown | Coadministration of voriconazole with REYATAZ, with or without ritonavir, has not been studied. Administration of voriconazole with ritonavir 100 mg every 12 hours decreased voriconazole steady-state AUC by an average of 39%. Voriconazole should not be administered to patients receiving REYATAZ/ritonavir, unless an assessment of the benefit/risk to the patient justifies the use of voriconazole. Coadministration of voriconazole with REYATAZ (without ritonavir) may increase atazanavir concentrations; however, no data are available.
Antigout: colchicine | ↑ colchicine | REYATAZ should not be coadministered with colchicine to patients with renal or hepatic impairment. Recommended dosage of colchicine when administered with REYATAZ: Treatment of gout flares:; 0.6 mg (1 tablet) for 1 dose, followed by 0.3 mg (half tablet) 1 hour later. Not to be repeated before 3 days.; Prophylaxis of gout flares:; If the original regimen was 0.6 mg twice a day, the regimen should be adjusted to 0.3 mg once a day. If the original regimen was 0.6 mg once a day, the regimen should be adjusted to 0.3 mg once every other day.; Treatment of familial Mediterranean fever (FMF):; Maximum daily dose of 0.6 mg (may be given as 0.3 mg twice a day).
Antimycobacterials: rifabutin | ↑ rifabutin | A rifabutin dose reduction of up to 75% (eg, 150 mg every other day or 3 times per week) is recommended. Increased monitoring for rifabutin-associated adverse reactions including neutropenia is warranted.
Benzodiazepines: parenterally administered midazolamb | ↑ midazolam | Concomitant use of parenteral midazolam with REYATAZ may increase plasma concentrations of midazolam. Coadministration should be done in a setting which ensures close clinical monitoring and appropriate medical management in case of respiratory depression and/or prolonged sedation. Dosage reduction for midazolam should be considered, especially if more than a single dose of midazolam is administered. Coadministration of oral midazolam with REYATAZ is CONTRAINDICATED.
Calcium channel blockers: diltiazem | ↑ diltiazem and desacetyl-diltiazem | Caution is warranted. A dose reduction of diltiazem by 50% should be considered. ECG monitoring is recommended. Coadministration of REYATAZ/ritonavir with diltiazem has not been studied.
eg, felodipine, nifedipine, nicardipine, and verapamil | ↑ calcium channel blocker | Caution is warranted. Dose titration of the calcium channel blocker should be considered. ECG monitoring is recommended.
Endothelin receptor antagonists: bosentan | ↓ atazanavir ↑ bosentan | Plasma concentrations of atazanavir may be decreased when bosentan is administered with REYATAZ without ritonavir. Coadministration of bosentan and REYATAZ without ritonavir is not recommended. Coadministration of bosentan in patients on REYATAZ/ritonavir:; For patients who have been receiving REYATAZ/ritonavir for at least 10 days, start bosentan at 62.5 mg once daily or every other day based on individual tolerability.; Coadministration of REYATAZ/ritonavir in patients on bosentan:; Discontinue bosentan at least 36 hours before starting REYATAZ/ritonavir. At least 10 days after starting REYATAZ/ritonavir, resume bosentan at 62.5 mg once daily or every other day based on individual tolerability.
HMG-CoA reductase inhibitors: atorvastatin, rosuvastatin | ↑ atorvastatin ↑ rosuvastatin | Use the lowest possible dose of atorvastatin or rosuvastatin with careful monitoring, or consider other HMG-CoA reductase inhibitors such as pravastatin or fluvastatin in combination with REYATAZ (with or without ritonavir). The risk of myopathy, including rhabdomyolysis, may be increased when HIV protease inhibitors, including REYATAZ, are used in combination with these drugs.
H2-Receptor antagonists | ↓ atazanavir | Plasma concentrations of atazanavir were substantially decreased when REYATAZ 400 mg once daily was administered simultaneously with famotidine 40 mg twice daily, which may result in loss of therapeutic effect and development of resistance.
 |  | In treatment-naive patients: REYATAZ 300 mg with ritonavir 100 mg once daily with food should be administered simultaneously with, and/or at least 10 hours after, a dose of the H2-receptor antagonist. An H2-receptor antagonist dose comparable to famotidine 20 mg once daily up to a dose comparable to famotidine 40 mg twice daily can be used with REYATAZ 300 mg with ritonavir 100 mg in treatment-naive patients. OR For patients unable to tolerate ritonavir, REYATAZ 400 mg once daily with food should be administered at least 2 hours before and at least 10 hours after a dose of the H2-receptor antagonist. No single dose of the H2-receptor antagonist should exceed a dose comparable to famotidine 20 mg, and the total daily dose should not exceed a dose comparable to famotidine 40 mg. However, REYATAZ should not be used without ritonavir in pregnant women.
 |  | In treatment-experienced patients: Whenever an H2-receptor antagonist is given to a patient receiving REYATAZ with ritonavir, the H2-receptor antagonist dose should not exceed a dose comparable to famotidine 20 mg twice daily, and the REYATAZ and ritonavir doses should be administered simultaneously with, and/or at least 10 hours after, the dose of the H2-receptor antagonist.; - REYATAZ 300 mg with ritonavir 100 mg once daily (all as a single dose with food) if taken with an H2-receptor antagonist. For pregnant women taking REYATAZ with ritonavir and an H2-receptor antagonist, see Dosage and Administration (2.3). - REYATAZ 400 mg with ritonavir 100 mg once daily (all as a single dose with food) if taken with both tenofovir and an H2-receptor antagonist. For pregnant women taking REYATAZ with ritonavir and both tenofovir and an H2-receptor antagonist, see Dosage and Administration (2.3).
Hormonal contraceptives: ethinyl estradiol and norgestimate or norethindrone | ↓ ethinyl estradiol ↑ norgestimatec ↑ ethinyl estradiol ↑ norethindroned | Use with caution if coadministration of REYATAZ or REYATAZ/ritonavir with oral contraceptives is considered. If an oral contraceptive is administered with REYATAZ plus ritonavir, it is recommended that the oral contraceptive contain at least 35 mcg of ethinyl estradiol. If REYATAZ is administered without ritonavir, the oral contraceptive should contain no more than 30 mcg of ethinyl estradiol. Potential safety risks include substantial increases in progesterone exposure. The long-term effects of increases in concentration of the progestational agent are unknown and could increase the risk of insulin resistance, dyslipidemia, and acne. Coadministration of REYATAZ or REYATAZ/ritonavir with other hormonal contraceptives (eg, contraceptive patch, contraceptive vaginal ring, or injectable contraceptives) or oral contraceptives containing progestogens other than norethindrone or norgestimate, or less than 25 mcg of ethinyl estradiol, has not been studied; therefore, alternative methods of contraception are recommended.
Immunosuppressants: cyclosporin, sirolimus, tacrolimus | ↑ immunosuppressants | Therapeutic concentration monitoring is recommended for immunosuppressant agents when coadministered with REYATAZ (atazanavir sulfate).
Inhaled beta agonist: salmeterol | ↑ salmeterol | Coadministration of salmeterol with REYATAZ is not recommended. Concomitant use of salmeterol and REYATAZ may result in increased risk of cardiovascular adverse events associated with salmeterol, including QT prolongation, palpitations, and sinus tachycardia.
Inhaled/nasal steroid: fluticasone | REYATAZ ↑ fluticasone | Concomitant use of fluticasone propionate and REYATAZ (without ritonavir) may increase plasma concentrations of fluticasone propionate. Use with caution. Consider alternatives to fluticasone propionate, particularly for long-term use.
 | REYATAZ/ritonavir ↑ fluticasone | Concomitant use of fluticasone propionate and REYATAZ/ritonavir may increase plasma concentrations of fluticasone propionate, resulting in significantly reduced serum cortisol concentrations. Systemic corticosteroid effects, including Cushing’s syndrome and adrenal suppression, have been reported during postmarketing use in patients receiving ritonavir and inhaled or intranasally administered fluticasone propionate. Coadministration of fluticasone propionate and REYATAZ/ritonavir is not recommended unless the potential benefit to the patient outweighs the risk of systemic corticosteroid side effects [see Warnings and Precautions (5.1)].
Macrolide antibiotics: clarithromycin | ↑ clarithromycin ↓ 14-OH clarithromycin ↑ atazanavir | Increased concentrations of clarithromycin may cause QTc prolongations; therefore, a dose reduction of clarithromycin by 50% should be considered when it is coadministered with REYATAZ. In addition, concentrations of the active metabolite 14-OH clarithromycin are significantly reduced; consider alternative therapy for indications other than infections due to Mycobacterium avium complex. Coadministration of REYATAZ/ritonavir with clarithromycin has not been studied.
Opioids: Buprenorphine | ↑ buprenorphine ↑ norbuprenorphine | Coadministration of buprenorphine and REYATAZ with or without ritonavir increases the plasma concentration of buprenorphine and norbuprenorphine. Coadministration of REYATAZ plus ritonavir with buprenorphine warrants clinical monitoring for sedation and cognitive effects. A dose reduction of buprenorphine may be considered. Coadministration of buprenorphine and REYATAZ with ritonavir is not expected to decrease atazanavir plasma concentrations. Coadministration of buprenorphine and REYATAZ without ritonavir may decrease atazanavir plasma concentrations. REYATAZ without ritonavir should not be coadministered with buprenorphine.
PDE5 inhibitors: sildenafil, tadalafil, vardenafil | ↑ sildenafil ↑ tadalafil ↑ vardenafil | Coadministration with REYATAZ has not been studied but may result in an increase in PDE5 inhibitor-associated adverse events, including hypotension, syncope, visual disturbances, and priapism. Use of PDE5 inhibitors for pulmonary arterial hypertension (PAH):; Use of REVATIO® (sildenafil) for the treatment of pulmonary hypertension (PAH) is contraindicated with REYATAZ [see Contraindications (4)]. The following dose adjustments are recommended for the use of ADCIRCA® (tadalafil) with REYATAZ: Coadministration of ADCIRCA® in patients on REYATAZ (with or without ritonavir): - For patients receiving REYATAZ (with or without ritonavir) for at least one week, start ADCIRCA® at 20 mg once daily. Increase to 40 mg once daily based on individual tolerability. Coadministration of REYATAZ (with or without ritonavir) in patients on ADCIRCA®: - Avoid the use of ADCIRCA® when starting REYATAZ (with or without ritonavir). Stop ADCIRCA® at least 24 hours before starting REYATAZ (with or without ritonavir). At least one week after starting REYATAZ (with or without ritonavir), resume ADCIRCA® at 20 mg once daily. Increase to 40 mg once daily based on individual tolerability.
 |  | Use of PDE5 inhibitors for erectile dysfunction:; Use VIAGRA® (sildenafil) with caution at reduced doses of 25 mg every 48 hours with increased monitoring for adverse events.; Use CIALIS® (tadalafil) with caution at reduced doses of 10 mg every 72 hours with increased monitoring for adverse events.; REYATAZ/ritonavir: Use LEVITRA® (vardenafil) with caution at reduced doses of no more than 2.5 mg every 72 hours with increased monitoring for adverse events.; REYATAZ: Use LEVITRA® (vardenafil) with caution at reduced doses of no more than 2.5 mg every 24 hours with increased monitoring for adverse events.
Proton-pump inhibitors: omeprazole | ↓ atazanavir | Plasma concentrations of atazanavir were substantially decreased when REYATAZ 400 mg or REYATAZ 300 mg/ritonavir 100 mg once daily was administered with omeprazole 40 mg once daily, which may result in loss of therapeutic effect and development of resistance.
 |  | In treatment-naive patients: The proton-pump inhibitor dose should not exceed a dose comparable to omeprazole 20 mg and must be taken approximately 12 hours prior to the REYATAZ 300 mg with ritonavir 100 mg dose.
 |  | In treatment-experienced patients: Proton-pump inhibitors should not be used in treatment-experienced patients receiving REYATAZ.
a For magnitude of interactions see Clinical Pharmacology, Tables 17 and 18 (12.3).
b See Contraindications (4), Table 3 for orally administered midazolam.
c In combination with atazanavir 300 mg and ritonavir 100 mg once daily.
d In combination with atazanavir 400 mg once daily.

7.4 Drugs with No Observed or Predicted Interactions with REYATAZ

Clinically significant interactions are not expected between atazanavir and substrates of CYP2C19, CYP2C9, CYP2D6, CYP2B6, CYP2A6, CYP1A2, or CYP2E1. Clinically significant interactions are not expected between atazanavir when administered with ritonavir and substrates of CYP2C8. See the complete prescribing information for NORVIR® for information on other potential drug interactions with ritonavir.

Based on known metabolic profiles, clinically significant drug interactions are not expected between REYATAZ (atazanavir sulfate) and fluvastatin, pravastatin, dapsone, trimethoprim/sulfamethoxazole, azithromycin, or erythromycin. REYATAZ does not interact with substrates of CYP2D6 (eg, nortriptyline, desipramine, metoprolol). Additionally, no clinically significant drug interactions were observed when REYATAZ was coadministered with methadone, fluconazole, acetaminophen, or atenolol. [See Clinical Pharmacology, Tables 17 and 18 (12.3).]

8 USE IN SPECIFIC POPULATIONS

8.1 Pregnancy

TERATOGENIC EFFECTS

Pregnancy Category B

Antiretroviral Pregnancy Registry: To monitor maternal-fetal outcomes of pregnant women exposed to REYATAZ, an Antiretroviral Pregnancy Registry has been established. Physicians are encouraged to register patients by calling 1-800-258-4263.

TERATOGENIC EFFECTS

Risk Summary

Atazanavir has been evaluated in a limited number of women during pregnancy and postpartum. Available human and animal data suggest that atazanavir does not increase the risk of major birth defects overall compared to the background rate. However, because the studies in humans cannot rule out the possibility of harm, REYATAZ should be used during pregnancy only if clearly needed.

Cases of lactic acidosis syndrome, sometimes fatal, and symptomatic hyperlactatemia have occurred in pregnant women using REYATAZ in combination with nucleoside analogues. Nucleoside analogues are associated with an increased risk of lactic acidosis syndrome.

Hyperbilirubinemia occurs frequently in patients who take REYATAZ, including pregnant women. All infants, including neonates exposed to REYATAZ in-utero, should be monitored for the development of severe hyperbilirubinemia during the first few days of life.

TERATOGENIC EFFECTS

Clinical Considerations

Dosing During Pregnancy and the Postpartum Period:

- REYATAZ should not be administered without ritonavir.
- REYATAZ should only be administered to pregnant women with HIV-1 strains susceptible to atazanavir.
- For pregnant patients, no dose adjustment is required for REYATAZ with the following exceptions:
  - For treatment-experienced pregnant women during the second or third trimester, when REYATAZ is coadministered with either an H2-receptor antagonist or tenofovir, REYATAZ 400 mg with ritonavir 100 mg once daily is recommended. There are insufficient data to recommend a REYATAZ dose for use with both an H2-receptor antagonist and tenofovir in treatment-experienced pregnant women.
- No dose adjustment is required for postpartum patients. However, patients should be closely monitored for adverse events because atazanavir exposures could be higher during the first 2 months after delivery. [See Dosage and Administration (2, 2.3) and Clinical Pharmacology (12.3).]

TERATOGENIC EFFECTS

Human Data

Clinical Trials: In clinical trial AI424-182, REYATAZ/ritonavir (300/100 mg or 400/100 mg) in combination with zidovudine/lamivudine was administered to 41 HIV-infected pregnant women during the second or third trimester. Among the 39 women who completed the study, 38 women achieved an HIV RNA <50 copies/mL at time of delivery. Six of 20 (30%) women on REYATAZ/ritonavir 300/100 mg and 13 of 21 (62%) women on REYATAZ/ritonavir 400/100 mg experienced hyperbilirubinemia (total bilirubin greater than or equal to 2.6 times the upper limit of normal). There were no cases of lactic acidosis observed in clinical trial AI424-182.

Atazanavir drug concentrations in fetal umbilical cord blood were approximately 12–19% of maternal concentrations. Among the 40 infants born to 40 HIV-infected pregnant women, all had test results that were negative for HIV-1 DNA at the time of delivery and/or during the first 6 months postpartum. All 40 infants received antiretroviral prophylactic treatment containing zidovudine. No evidence of severe hyperbilirubinemia (total bilirubin levels greater than 20 mg/dL) or acute or chronic bilirubin encephalopathy was observed among neonates in this study. However, 10/36 (28%) infants (6 greater than or equal to 38 weeks gestation and 4 less than 38 weeks gestation) had bilirubin levels of 4 mg/dL or greater within the first day of life.

Lack of ethnic diversity was a study limitation. In the study population, 33/40 (83%) infants were Black/African American, who have a lower incidence of neonatal hyperbilirubinemia than Caucasians and Asians. In addition, women with Rh incompatibility were excluded, as well as women who had a previous infant who developed hemolytic disease and/or had neonatal pathologic jaundice (requiring phototherapy).

Additionally, of the 38 infants who had glucose samples collected in the first day of life, 3 had adequately collected serum glucose samples with values of <40 mg/dL that could not be attributed to maternal glucose intolerance, difficult delivery, or sepsis.

Antiretroviral Pregnancy Registry Data: As of January 2010, the Antiretroviral Pregnancy Registry (APR) has received prospective reports of 635 exposures to atazanavir-containing regimens (425 exposed in the first trimester and 160 and 50 exposed in second and third trimester, respectively). Birth defects occurred in 9 of 393 (2.3%) live births (first trimester exposure) and 5 of 212 (2.4%) live births (second/third trimester exposure). Among pregnant women in the U.S. reference population, the background rate of birth defects is 2.7%. There was no association between atazanavir and overall birth defects observed in the APR.

TERATOGENIC EFFECTS

Pharmacokinetics of Atazanavir in Pregnancy

[See Clinical Pharmacology (12.3).]

TERATOGENIC EFFECTS

Animal Data

In animal reproduction studies, there was no evidence of teratogenicity in offspring born to animals at systemic drug exposure levels (AUC) 0.7 (in rabbits) to 1.2 (in rats) times those observed at the human clinical dose (300 mg/day atazanavir boosted with 100 mg/day ritonavir). In pre- and post-natal development studies in the rat, atazanavir caused body weight loss or weight gain suppression in the animal offspring with maternal drug exposure (AUC) 1.3 times the human exposure at this clinical dose. However, maternal toxicity also occurred at this exposure level.

8.3 Nursing Mothers

The Centers for Disease Control and Prevention recommend that HIV-infected mothers not breast-feed their infants to avoid risking postnatal transmission of HIV. It is not known whether atazanavir is present in human milk. Because of both the potential for HIV transmission and the potential for serious adverse reactions in nursing infants, mothers should be instructed not to breast-feed if they are taking REYATAZ.

8.4 Pediatric Use

REYATAZ should not be administered to pediatric patients below the age of 3 months due to the risk of kernicterus.

The safety, activity, and pharmacokinetic profiles of REYATAZ in pediatric patients ages 3 months to less than 6 years have not been established.

The safety, pharmacokinetic profile, and virologic response of REYATAZ were evaluated in pediatric patients in an open-label, multicenter clinical trial PACTG 1020A [see Clinical Pharmacology (12.3) and Clinical Studies (14.3)]. The safety profile in pediatric patients was generally similar to that observed in adults [see Adverse Reactions (6.2)]. Please see Dosage and Administration (2.2) for dosing recommendations for pediatric patients 6 years of age and older.

8.5 Geriatric Use

Clinical studies of REYATAZ did not include sufficient numbers of patients aged 65 and over to determine whether they respond differently from younger patients. Based on a comparison of mean single-dose pharmacokinetic values for Cmax and AUC, a dose adjustment based upon age is not recommended. In general, appropriate caution should be exercised in the administration and monitoring of REYATAZ in elderly patients reflecting the greater frequency of decreased hepatic, renal, or cardiac function, and of concomitant disease or other drug therapy.

8.6 Age/Gender

A study of the pharmacokinetics of atazanavir was performed in young (n=29; 18–40 years) and elderly (n=30; ≥65 years) healthy subjects. There were no clinically important pharmacokinetic differences observed due to age or gender.

8.7 Impaired Renal Function

In healthy subjects, the renal elimination of unchanged atazanavir was approximately 7% of the administered dose. REYATAZ has been studied in adult subjects with severe renal impairment (n=20), including those on hemodialysis, at multiple doses of 400 mg once daily. The mean atazanavir Cmax was 9% lower, AUC was 19% higher, and Cmin was 96% higher in subjects with severe renal impairment not undergoing hemodialysis (n=10), than in age, weight, and gender matched subjects with normal renal function. Atazanavir was not appreciably cleared during hemodialysis. In a 4-hour dialysis session, 2.1% of the administered dose was removed. When atazanavir was administered either prior to, or following hemodialysis (n=10), the geometric means for Cmax, AUC, and Cmin were approximately 25 to 43% lower compared to subjects with normal renal function. The mechanism of this decrease is unknown. REYATAZ should not be administered to HIV-treatment-experienced patients with end stage renal disease managed with hemodialysis. [See Dosage and Administration (2.4).]

8.8 Impaired Hepatic Function

Atazanavir is metabolized and eliminated primarily by the liver. REYATAZ (atazanavir sulfate) has been studied in adult subjects with moderate to severe hepatic impairment (14 Child-Pugh B and 2 Child-Pugh C subjects) after a single 400-mg dose. The mean AUC(0-∞) was 42% greater in subjects with impaired hepatic function than in healthy volunteers. The mean half-life of atazanavir in hepatically impaired subjects was 12.1 hours compared to 6.4 hours in healthy volunteers. Increased concentrations of atazanavir are expected in patients with moderately or severely impaired hepatic function. The pharmacokinetics of REYATAZ in combination with ritonavir have not been studied in subjects with hepatic impairment. REYATAZ should not be administered to patients with severe hepatic impairment. REYATAZ/ritonavir is not recommended for use in patients with hepatic impairment. [See Dosage and Administration (2.5) and Warnings and Precautions (5.5).]

10 OVERDOSAGE

Human experience of acute overdose with REYATAZ is limited. Single doses up to 1200 mg have been taken by healthy volunteers without symptomatic untoward effects. A single self-administered overdose of 29.2 g of REYATAZ in an HIV-infected patient (73 times the 400-mg recommended dose) was associated with asymptomatic bifascicular block and PR interval prolongation. These events resolved spontaneously. At high doses that lead to high drug exposures, jaundice due to indirect (unconjugated) hyperbilirubinemia (without associated liver function test changes) or PR interval prolongation may be observed. [See Warnings and Precautions (5.2, 5.4) and Clinical Pharmacology (12.2).]

Treatment of overdosage with REYATAZ should consist of general supportive measures, including monitoring of vital signs and ECG, and observations of the patient’s clinical status. If indicated, elimination of unabsorbed atazanavir should be achieved by emesis or gastric lavage. Administration of activated charcoal may also be used to aid removal of unabsorbed drug. There is no specific antidote for overdose with REYATAZ. Since atazanavir is extensively metabolized by the liver and is highly protein bound, dialysis is unlikely to be beneficial in significant removal of this medicine.

11 DESCRIPTION

REYATAZ® (atazanavir sulfate) is an azapeptide inhibitor of HIV-1 protease.

The chemical name for atazanavir sulfate is (3S,8S,9S,12S)-3,12-Bis(1,1-dimethylethyl)-8-hydroxy-4,11-dioxo-9-(phenylmethyl)-6-[[4-(2-pyridinyl)phenyl]methyl]-2,5,6,10,13-pentaazatetradecanedioic acid dimethyl ester, sulfate (1:1). Its molecular formula is C38H52N6O7•H2SO4, which corresponds to a molecular weight of 802.9 (sulfuric acid salt). The free base molecular weight is 704.9. Atazanavir sulfate has the following structural formula:

Atazanavir sulfate is a white to pale yellow crystalline powder. It is slightly soluble in water (4–5 mg/mL, free base equivalent) with the pH of a saturated solution in water being about 1.9 at 24 ± 3° C.

REYATAZ Capsules are available for oral administration in strengths containing the equivalent of 100 mg, 150 mg, 200 mg, or 300 mg of atazanavir as atazanavir sulfate and the following inactive ingredients: crospovidone, lactose monohydrate, and magnesium stearate. The capsule shells contain the following inactive ingredients: gelatin, FD&C Blue #2, titanium dioxide, black iron oxide, red iron oxide, and yellow iron oxide. The capsules are printed with ink containing shellac, titanium dioxide, FD&C Blue #2, isopropyl alcohol, ammonium hydroxide, propylene glycol, n-butyl alcohol, simethicone, and dehydrated alcohol.

12 CLINICAL PHARMACOLOGY

12.1 Mechanism of Action

Atazanavir is an antiviral drug [see Clinical Pharmacology (12.4)].

12.2 Pharmacodynamics

Effects on Electrocardiogram

Concentration- and dose-dependent prolongation of the PR interval in the electrocardiogram has been observed in healthy volunteers receiving atazanavir. In a placebo-controlled study (AI424-076), the mean (±SD) maximum change in PR interval from the predose value was 24 (±15) msec following oral dosing with 400 mg of atazanavir (n=65) compared to 13 (±11) msec following dosing with placebo (n=67). The PR interval prolongations in this study were asymptomatic. There is limited information on the potential for a pharmacodynamic interaction in humans between atazanavir and other drugs that prolong the PR interval of the electrocardiogram. [See Warnings and Precautions (5.2).]

Electrocardiographic effects of atazanavir were determined in a clinical pharmacology study of 72 healthy subjects. Oral doses of 400 mg and 800 mg were compared with placebo; there was no concentration-dependent effect of atazanavir on the QTc interval (using Fridericia’s correction). In 1793 HIV-infected patients receiving antiretroviral regimens, QTc prolongation was comparable in the atazanavir and comparator regimens. No atazanavir-treated healthy subject or HIV-infected patient in clinical trials had a QTc interval >500 msec. [See Warnings and Precautions (5.2).]

In a pharmacokinetic study between atazanavir 400 mg once daily and diltiazem 180 mg once daily, a CYP3A substrate, there was a 2-fold increase in the diltiazem plasma concentration and an additive effect on the PR interval. In a pharmacokinetic study between atazanavir 400 mg once daily and atenolol 50 mg once daily, there was no substantial additive effect of atazanavir and atenolol on the PR interval. [See Warnings and Precautions (5.2).]

12.3 Pharmacokinetics

The pharmacokinetics of atazanavir were evaluated in healthy adult volunteers and in HIV-infected patients after administration of REYATAZ 400 mg once daily and after administration of REYATAZ 300 mg with ritonavir 100 mg once daily (see Table 14).

Table 14: Steady-State Pharmacokinetics of Atazanavir in Healthy Subjects or HIV-Infected Patients in the Fed State
 | 400 mg once daily |  | 300 mg with ritonavir 100 mg once daily
Parameter | Healthy Subjects (n=14) | HIV-Infected Patients (n=13) | Healthy Subjects (n=28) | HIV-Infected Patients (n=10)
Cmax (ng/mL)
Geometric mean (CV%) | 5199 (26) | 2298 (71) | 6129 (31) | 4422 (58)
Mean (SD) | 5358 (1371) | 3152 (2231) | 6450 (2031) | 5233 (3033)
Tmax (h)
Median | 2.5 | 2.0 | 2.7 | 3.0
AUC (ng•h/mL)
Geometric mean (CV%) | 28132 (28) | 14874 (91) | 57039 (37) | 46073 (66)
Mean (SD) | 29303 (8263) | 22262 (20159) | 61435 (22911) | 53761 (35294)
T-half (h)
Mean (SD) | 7.9 (2.9) | 6.5 (2.6) | 18.1 (6.2)a | 8.6 (2.3)
Cmin (ng/mL)
Geometric mean (CV%) | 159 (88) | 120 (109) | 1227 (53) | 636 (97)
Mean (SD) | 218 (191) | 273 (298)b | 1441 (757) | 862 (838)
a n=26.
b n=12.

Figure 1 displays the mean plasma concentrations of atazanavir at steady state after REYATAZ 400 mg once daily (as two 200-mg capsules) with a light meal and after REYATAZ 300 mg (as two 150-mg capsules) with ritonavir 100 mg once daily with a light meal in HIV-infected adult patients.

Figure 1: Mean (SD) Steady-State Plasma Concentrations of Atazanavir 400 mg (n=13) and 300 mg with Ritonavir (n=10) for HIV-Infected Adult Patients

Absorption

Atazanavir is rapidly absorbed with a Tmax of approximately 2.5 hours. Atazanavir demonstrates nonlinear pharmacokinetics with greater than dose-proportional increases in AUC and Cmax values over the dose range of 200–800 mg once daily. Steady state is achieved between Days 4 and 8, with an accumulation of approximately 2.3-fold.

Food Effect

Administration of REYATAZ with food enhances bioavailability and reduces pharmacokinetic variability. Administration of a single 400-mg dose of REYATAZ with a light meal (357 kcal, 8.2 g fat, 10.6 g protein) resulted in a 70% increase in AUC and 57% increase in Cmax relative to the fasting state. Administration of a single 400-mg dose of REYATAZ with a high-fat meal (721 kcal, 37.3 g fat, 29.4 g protein) resulted in a mean increase in AUC of 35% with no change in Cmax relative to the fasting state. Administration of REYATAZ (atazanavir sulfate) with either a light meal or high-fat meal decreased the coefficient of variation of AUC and Cmax by approximately one-half compared to the fasting state.

Coadministration of a single 300-mg dose of REYATAZ and a 100-mg dose of ritonavir with a light meal (336 kcal, 5.1 g fat, 9.3 g protein) resulted in a 33% increase in the AUC and a 40% increase in both the Cmax and the 24-hour concentration of atazanavir relative to the fasting state. Coadministration with a high-fat meal (951 kcal, 54.7 g fat, 35.9 g protein) did not affect the AUC of atazanavir relative to fasting conditions and the Cmax was within 11% of fasting values. The 24-hour concentration following a high-fat meal was increased by approximately 33% due to delayed absorption; the median Tmax increased from 2.0 to 5.0 hours. Coadministration of REYATAZ with ritonavir with either a light or a high-fat meal decreased the coefficient of variation of AUC and Cmax by approximately 25% compared to the fasting state.

Distribution

Atazanavir is 86% bound to human serum proteins and protein binding is independent of concentration. Atazanavir binds to both alpha-1-acid glycoprotein (AAG) and albumin to a similar extent (89% and 86%, respectively). In a multiple-dose study in HIV-infected patients dosed with REYATAZ 400 mg once daily with a light meal for 12 weeks, atazanavir was detected in the cerebrospinal fluid and semen. The cerebrospinal fluid/plasma ratio for atazanavir (n=4) ranged between 0.0021 and 0.0226 and seminal fluid/plasma ratio (n=5) ranged between 0.11 and 4.42.

Metabolism

Atazanavir is extensively metabolized in humans. The major biotransformation pathways of atazanavir in humans consisted of monooxygenation and dioxygenation. Other minor biotransformation pathways for atazanavir or its metabolites consisted of glucuronidation, N-dealkylation, hydrolysis, and oxygenation with dehydrogenation. Two minor metabolites of atazanavir in plasma have been characterized. Neither metabolite demonstrated in vitro antiviral activity. In vitro studies using human liver microsomes suggested that atazanavir is metabolized by CYP3A.

Elimination

Following a single 400-mg dose of ^14C-atazanavir, 79% and 13% of the total radioactivity was recovered in the feces and urine, respectively. Unchanged drug accounted for approximately 20% and 7% of the administered dose in the feces and urine, respectively. The mean elimination half-life of atazanavir in healthy volunteers (n=214) and HIV-infected adult patients (n=13) was approximately 7 hours at steady state following a dose of 400 mg daily with a light meal.

Special Populations

Pediatrics

The pharmacokinetic parameters for atazanavir at steady state in pediatric patients were predicted by a population pharmacokinetic model and are summarized in Table 15 by weight ranges that correspond to the recommended doses. [See Dosage and Administration (2.2).]

Table 15: Predicted Steady-State Pharmacokinetics of Atazanavir (capsule formulation) with ritonavir in HIV-Infected Pediatric Patients
Body Weight (range in kg) | atazanavir/ritonavir Dose (mg) | Cmax ng/mL Geometric Mean (CV%) | AUC ng•h/mL Geometric Mean (CV%) | Cmin ng/mL Geometric Mean (CV%)
15–<20 | 150/100 | 5213 (78.7%) | 42902 (77.0%) | 504 (99.5%)
20–<40 | 200/100 | 4954 (81.7%) | 42999 (78.5%) | 562 (98.9%)
≥40 | 300/100 | 5040 (84.6%) | 46777 (80.6%) | 691 (98.5%)

Pregnancy

The pharmacokinetic data from HIV-infected pregnant women receiving REYATAZ Capsules with ritonavir are presented in Table 16.

Table 16: Steady-State Pharmacokinetics of Atazanavir with ritonavir in HIV-Infected Pregnant Women in the Fed State
 | Atazanavir 300 mg with ritonavir 100 mg
Pharmacokinetic Parameter | 2nd Trimester (n=5a) | 3rd Trimester (n=20) | Postpartumb (n=34)
Cmax ng/mL | 3078.85 | 3291.46 | 5721.21
Geometric mean (CV%) | (50) | (48) | (31)
AUC ng∙h/mL | 27657.1 | 34251.5 | 61990.4
Geometric mean (CV%) | (43) | (43) | (32)
Cmin ng/mLc | 538.70 | 668.48 | 1462.59
Geometric mean (CV%) | (46) | (50) | (45)
a Available data during the 2nd trimester are limited.
b Atazanavir peak concentrations and AUCs were found to be approximately 28–43% higher during the postpartum period (4–12 weeks) than those observed historically in HIV-infected, non-pregnant patients. Atazanavir plasma trough concentrations were approximately 2.2-fold higher during the postpartum period when compared to those observed historically in HIV-infected, non-pregnant patients.
c Cmin is concentration 24 hours post-dose.

Drug Interaction Data

Atazanavir is a metabolism-dependent CYP3A inhibitor, with a Kinact value of 0.05 to 0.06 min^-1 and Ki value of 0.84 to 1.0 µM. Atazanavir is also a direct inhibitor for UGT1A1 (Ki=1.9 µM) and CYP2C8 (Ki=2.1 µM).

Atazanavir has been shown in vivo not to induce its own metabolism, nor to increase the biotransformation of some drugs metabolized by CYP3A. In a multiple-dose study, REYATAZ decreased the urinary ratio of endogenous 6β-OH cortisol to cortisol versus baseline, indicating that CYP3A production was not induced.

Drug interaction studies were performed with REYATAZ and other drugs likely to be coadministered and some drugs commonly used as probes for pharmacokinetic interactions. The effects of coadministration of REYATAZ on the AUC, Cmax, and Cmin are summarized in Tables 17 and 18. For information regarding clinical recommendations, see Drug Interactions (7).

Table 17: Drug Interactions: Pharmacokinetic Parameters for Atazanavir in the Presence of Coadministered Drugsa
Coadministered Drug | Coadministered Drug Dose/Schedule | REYATAZ Dose/Schedule | Ratio (90% Confidence Interval) of Atazanavir Pharmacokinetic Parameters with/without Coadministered Drug; No Effect = 1.00
Coadministered Drug | Coadministered Drug Dose/Schedule | REYATAZ Dose/Schedule | Cmax | AUC | Cmin
atenolol | 50 mg QD, d 7−11 (n=19) and d 19−23 | 400 mg QD, d 1−11 (n=19) | 1.00 (0.89, 1.12) | 0.93 (0.85, 1.01) | 0.74 (0.65, 0.86)
clarithromycin | 500 mg BID, d 7−10 (n=29) and d 18−21 | 400 mg QD, d 1−10 (n=29) | 1.06 (0.93, 1.20) | 1.28 (1.16, 1.43) | 1.91 (1.66, 2.21)
didanosine (ddI) (buffered tablets) plus stavudine (d4T)b | ddI: 200 mg x 1 dose, d4T: 40 mg x 1 dose (n=31) | 400 mg x 1 dose simultaneously with ddI and d4T (n=31) | 0.11 (0.06, 0.18) | 0.13 (0.08, 0.21) | 0.16 (0.10, 0.27)
 | ddI: 200 mg x 1 dose, d4T: 40 mg x 1 dose (n=32) | 400 mg x 1 dose 1 h after ddI + d4T (n=32) | 1.12 (0.67, 1.18) | 1.03 (0.64, 1.67) | 1.03 (0.61, 1.73)
ddI (enteric-coated [EC] capsules)c | 400 mg d 8 (fed) (n=34) 400 mg d 19 (fed) (n=31) | 400 mg QD, d 2−8 (n=34) 300 mg/ritonavir 100 mg QD, d 9−19 (n=31) | 1.03 (0.93, 1.14) 1.04 (1.01, 1.07) | 0.99 (0.91, 1.08) 1.00 (0.96, 1.03) | 0.98 (0.89, 1.08) 0.87 (0.82, 0.92)
diltiazem | 180 mg QD, d 7−11 (n=30) and d 19−23 | 400 mg QD, d 1−11 (n=30) | 1.04 (0.96, 1.11) | 1.00 (0.95, 1.05) | 0.98 (0.90, 1.07)
efavirenz | 600 mg QD, d 7−20 (n=27) | 400 mg QD, d 1−20 (n=27) | 0.41 (0.33, 0.51) | 0.26 (0.22, 0.32) | 0.07 (0.05, 0.10)
 | 600 mg QD, d 7−20 (n=13) | 400 mg QD, d 1−6 (n=23) then 300 mg/ritonavir 100 mg QD, 2 h before efavirenz, d 7−20 (n=13) | 1.14 (0.83, 1.58) | 1.39 (1.02, 1.88) | 1.48 (1.24, 1.76)
 | 600 mg QD, d 11–24 (pm) (n=14) | 300 mg QD/ritonavir 100 mg QD, d 1–10 (pm) (n=22), then 400 mg QD/ritonavir 100 mg QD, d 11–24 (pm), (simultaneous with efavirenz) (n=14) | 1.17 (1.08, 1.27) | 1.00 (0.91, 1.10) | 0.58 (0.49, 0.69)
famotidine | 40 mg BID, d 7−12 (n=15) | 400 mg QD, d 1−6 (n=45), d 7−12 (simultaneous administration) (n=15) | 0.53 (0.34, 0.82) | 0.59 (0.40, 0.87) | 0.58 (0.37, 0.89)
 | 40 mg BID, d 7−12 (n=14) | 400 mg QD (pm), d 1−6 (n=14), d 7−12 (10 h after, 2 h before famotidine) (n=14) | 1.08 (0.82, 1.41) | 0.95 (0.74, 1.21) | 0.79 (0.60, 1.04)
 | 40 mg BID, d 11−20 (n=14)d | 300 mg QD/ritonavir 100 mg QD, d 1−10 (n=46), d 11−20d (simultaneous administration) (n=14) | 0.86 (0.79, 0.94) | 0.82 (0.75, 0.89) | 0.72 (0.64, 0.81)
 | 20 mg BID, d 11−17 (n=18) | 300 mg QD/ ritonavir 100 mg QD/tenofovir 300 mg QD, d 1−10 (am) (n=39), d 11−17 (am) (simultaneous administration with am famotidine) (n=18)e,f | 0.91 (0.84, 0.99) | 0.90 (0.82, 0.98) | 0.81 (0.69, 0.94)
 | 40 mg QD (pm), d 18−24 (n=20) | 300 mg QD/ ritonavir 100 mg QD/tenofovir 300 mg QD, d 1−10 (am) (n=39), d 18−24 (am) (12 h after pm famotidine) (n=20)f | 0.89 (0.81, 0.97) | 0.88 (0.80, 0.96) | 0.77 (0.63, 0.93)
 | 40 mg BID, d 18−24 (n=18) | 300 mg QD/ritonavir 100 mg QD/tenofovir 300 mg QD, d 1−10 (am) (n=39), d 18−24 (am) (10 h after pm famotidine and 2 h before am famotidine) (n=18)f | 0.74 (0.66, 0.84) | 0.79 (0.70, 0.88) | 0.72 (0.63, 0.83)
 | 40 mg BID, d 11−20 (n=15) | 300 mg QD/ritonavir 100 mg QD, d 1−10 (am) (n=46), then 400 mg QD/ritonavir 100 mg QD, d 11−20 (am) (n=15) | 1.02 (0.87, 1.18) | 1.03 (0.86, 1.22) | 0.86 (0.68, 1.08)
fluconazole | 200 mg QD, d 11−20 (n=29) | 300 mg QD/ ritonavir 100 mg QD, d 1−10 (n=19), d 11−20 (n=29) | 1.03 (0.95, 1.11) | 1.04 (0.95, 1.13) | 0.98 (0.85, 1.13)
ketoconazole | 200 mg QD, d 7−13 (n=14) | 400 mg QD, d 1−13 (n=14) | 0.99 (0.77, 1.28) | 1.10 (0.89, 1.37) | 1.03 (0.53, 2.01)
nevirapineg,h | 200 mg BID, d 1–23 (n=23) | 300 mg QD/ritonavir 100 mg QD, d 4–13, then 400 mg QD/ritonavir 100 mg QD, d 14–23 (n=23)i | 0.72 (0.60, 0.86) 1.02 (0.85, 1.24) | 0.58 (0.48, 0.71) 0.81 (0.65, 1.02) | 0.28 (0.20, 0.40) 0.41 (0.27, 0.60)
omeprazole | 40 mg QD, d 7−12 (n=16)j | 400 mg QD, d 1−6 (n=48), d 7−12 (n=16) | 0.04 (0.04, 0.05) | 0.06 (0.05, 0.07) | 0.05 (0.03, 0.07)
 | 40 mg QD, d 11−20 (n=15)j | 300 mg QD/ritonavir 100 mg QD, d 1−20 (n=15) | 0.28 (0.24, 0.32) | 0.24 (0.21, 0.27) | 0.22 (0.19, 0.26)
 | 20 mg QD, d 17−23 (am) (n=13) | 300 mg QD/ritonavir 100 mg QD, d 7−16 (pm) (n=27), d 17−23 (pm) (n=13)k,l | 0.61 (0.46, 0.81) | 0.58 (0.44, 0.75) | 0.54 (0.41, 0.71)
 | 20 mg QD, d 17−23 (am) (n=14) | 300 mg QD/ritonavir 100 mg QD, d 7−16 (am) (n=27), then 400 mg QD/ritonavir 100 mg QD, d 17−23 (am) (n=14)m,n | 0.69 (0.58, 0.83) | 0.70 (0.57, 0.86) | 0.69 (0.54, 0.88)
rifabutin | 150 mg QD, d 15−28 (n=7) | 400 mg QD, d 1−28 (n=7) | 1.34 (1.14, 1.59) | 1.15 (0.98, 1.34) | 1.13 (0.68, 1.87)
rifampin | 600 mg QD, d 17−26 (n=16) | 300 mg QD/ritonavir 100 mg QD, d 7−16 (n=48), d 17−26 (n=16) | 0.47 (0.41, 0.53) | 0.28 (0.25, 0.32) | 0.02 (0.02, 0.03)
ritonaviro | 100 mg QD, d 11−20 (n=28) | 300 mg QD, d 1−20 (n=28) | 1.86 (1.69, 2.05) | 3.38 (3.13, 3.63) | 11.89 (10.23, 13.82)
tenofovirp | 300 mg QD, d 9−16 (n=34) | 400 mg QD, d 2−16 (n=34) | 0.79 (0.73, 0.86) | 0.75 (0.70, 0.81) | 0.60 (0.52, 0.68)
 | 300 mg QD, d 15−42 (n=10) | 300 mg/ritonavir 100 mg QD, d 1−42 (n=10) | 0.72q (0.50, 1.05) | 0.75q (0.58, 0.97) | 0.77q (0.54, 1.10)
a Data provided are under fed conditions unless otherwise noted.
b All drugs were given under fasted conditions.
c 400 mg ddI EC and REYATAZ were administered together with food on Days 8 and 19.
d REYATAZ 300 mg plus ritonavir 100 mg once daily coadministered with famotidine 40 mg twice daily resulted in atazanavir geometric mean Cmax that was similar and AUC and Cmin values that were 1.79- and 4.46-fold higher relative to REYATAZ 400 mg once daily alone.
e Similar results were noted when famotidine 20 mg BID was administered 2 hours after and 10 hours before atazanavir 300 mg and ritonavir 100 mg plus tenofovir 300 mg.
f Atazanavir/ritonavir/tenofovir was administered after a light meal.
g Study was conducted in HIV-infected individuals.
h Compared with atazanavir 400 mg historical data without nevirapine (n=13), the ratio of geometric means (90% confidence intervals) for Cmax, AUC, and Cmin were 1.42 (0.98, 2.05), 1.64 (1.11, 2.42), and 1.25 (0.66, 2.36), respectively, for atazanavir/ritonavir 300/100 mg; and 2.02 (1.42, 2.87), 2.28 (1.54, 3.38), and 1.80 (0.94, 3.45), respectively, for atazanavir/ritonavir 400/100 mg.
i Parallel group design; n=23 for atazanavir/ritonavir plus nevirapine, n=22 for atazanavir 300 mg/ritonavir 100 mg without nevirapine. Subjects were treated with nevirapine prior to study entry.
j Omeprazole 40 mg was administered on an empty stomach 2 hours before REYATAZ.
k Omeprazole 20 mg was administered 30 minutes prior to a light meal in the morning and REYATAZ 300 mg plus ritonavir 100 mg in the evening after a light meal, separated by 12 hours from omeprazole.
l REYATAZ 300 mg plus ritonavir 100 mg once daily separated by 12 hours from omeprazole 20 mg daily resulted in increases in atazanavir geometric mean AUC (10%) and Cmin (2.4-fold), with a decrease in Cmax (29%) relative to REYATAZ 400 mg once daily in the absence of omeprazole (study days 1−6).
m Omeprazole 20 mg was given 30 minutes prior to a light meal in the morning and REYATAZ 400 mg plus ritonavir 100 mg once daily after a light meal, 1 hour after omeprazole. Effects on atazanavir concentrations were similar when REYATAZ 400 mg plus ritonavir 100 mg was separated from omeprazole 20 mg by 12 hours.
n REYATAZ 400 mg plus ritonavir 100 mg once daily administered with omeprazole 20 mg once daily resulted in increases in atazanavir geometric mean AUC (32%) and Cmin (3.3-fold), with a decrease in Cmax (26%) relative to REYATAZ 400 mg once daily in the absence of omeprazole (study days 1−6).
o Compared with atazanavir 400 mg QD historical data, administration of atazanavir/ritonavir 300/100 mg QD increased the atazanavir geometric mean values of Cmax, AUC, and Cmin by 18%, 103%, and 671%, respectively.
p Note that similar results were observed in studies where administration of tenofovir and REYATAZ was separated by 12 hours.
q Ratio of atazanavir plus ritonavir plus tenofovir to atazanavir plus ritonavir. Atazanavir 300 mg plus ritonavir 100 mg results in higher atazanavir exposure than atazanavir 400 mg (see footnote o). The geometric mean values of atazanavir pharmacokinetic parameters when coadministered with ritonavir and tenofovir were: Cmax = 3190 ng/mL, AUC = 34459 ng•h/mL, and Cmin = 491 ng/mL. Study was conducted in HIV-infected individuals.

Table 18: Drug Interactions: Pharmacokinetic Parameters for Coadministered Drugs in the Presence of REYATAZa
Coadministered Drug | Coadministered Drug Dose/Schedule | REYATAZ Dose/Schedule | Ratio (90% Confidence Interval) of Coadministered Drug Pharmacokinetic Parameters with/without REYATAZ; No Effect = 1.00
Coadministered Drug | Coadministered Drug Dose/Schedule | REYATAZ Dose/Schedule | Cmax | AUC | Cmin
acetaminophen | 1 gm BID, d 1−20 (n=10) | 300 mg QD/ritonavir 100 mg QD, d 11−20 (n=10) | 0.87 (0.77, 0.99) | 0.97 (0.91, 1.03) | 1.26 (1.08, 1.46)
atenolol | 50 mg QD, d 7−11 (n=19) and d 19−23 | 400 mg QD, d 1−11 (n=19) | 1.34 (1.26, 1.42) | 1.25 (1.16, 1.34) | 1.02 (0.88, 1.19)
clarithromycin | 500 mg BID, d 7−10 (n=21) and d 18−21 | 400 mg QD, d 1−10 (n=21) | 1.50 (1.32, 1.71) OH- clarithromycin: 0.28 (0.24, 0.33) | 1.94 (1.75, 2.16) OH- clarithromycin: 0.30 (0.26, 0.34) | 2.60 (2.35, 2.88) OH- clarithromycin: 0.38 (0.34, 0.42)
didanosine (ddI) (buffered tablets) plus stavudine (d4T)b | ddI: 200 mg x 1 dose, d4T: 40 mg x 1 dose (n=31) | 400 mg x 1 dose simultaneous with ddI and d4T (n=31) | ddI: 0.92 (0.84, 1.02) d4T: 1.08 (0.96, 1.22) | ddI: 0.98 (0.92, 1.05) d4T: 1.00 (0.97, 1.03) | NA d4T: 1.04 (0.94, 1.16)
ddI (enteric-coated [EC] capsules)c | 400 mg d 1 (fasted), d 8 (fed) (n=34) | 400 mg QD, d 2−8 (n=34) | 0.64 (0.55, 0.74) | 0.66 (0.60, 0.74) | 1.13 (0.91, 1.41)
 | 400 mg d 1 (fasted), d 19 (fed) (n=31) | 300 mg QD/ritonavir 100 mg QD, d 9−19 (n=31) | 0.62 (0.52, 0.74) | 0.66 (0.59, 0.73) | 1.25 (0.92, 1.69)
diltiazem | 180 mg QD, d 7−11 (n=28) and d 19−23 | 400 mg QD, d 1−11 (n=28) | 1.98 (1.78, 2.19) desacetyl- diltiazem: 2.72 (2.44, 3.03) | 2.25 (2.09, 2.16) desacetyl- diltiazem: 2.65 (2.45, 2.87) | 2.42 (2.14, 2.73) desacetyl- diltiazem: 2.21 (2.02, 2.42)
ethinyl estradiol & norethindroned | Ortho-Novum® 7/7/7 QD, d 1−29 (n=19) | 400 mg QD, d 16−29 (n=19) | ethinyl estradiol: 1.15 (0.99, 1.32) norethindrone: 1.67 (1.42, 1.96) | ethinyl estradiol: 1.48 (1.31, 1.68) norethindrone: 2.10 (1.68, 2.62) | ethinyl estradiol: 1.91 (1.57, 2.33) norethindrone: 3.62 (2.57, 5.09)
ethinyl estradiol & norgestimatee | Ortho Tri-Cyclen® QD, d 1–28 (n=18), then Ortho Tri-Cyclen® LO QD, d 29–42f (n=14) | 300 mg QD/ritonavir 100 mg QD, d 29–42 (n=14) | ethinyl estradiol: 0.84 (0.74, 0.95) 17-deacetyl norgestimate:g 1.68 (1.51, 1.88) | ethinyl estradiol: 0.81 (0.75, 0.87) 17-deacetyl norgestimate:g 1.85 (1.67, 2.05) | ethinyl estradiol: 0.63 (0.55, 0.71) 17-deacetyl norgestimate:g 2.02 (1.77, 2.31)
fluconazole | 200 mg QD, d 1−10 (n=11) and 200 mg QD, d 11−20 (n=29) | 300 mg QD/ritonavir 100 mg QD, d 11−20 (n=29) | 1.05 (0.99, 1.10) | 1.08 (1.02, 1.15) | 1.07 (1.00, 1.15)
methadone | Stable maintenance dose, d 1−15 (n=16) | 400 mg QD, d 2−15 (n=16) | (R)- methadoneh 0.91 (0.84, 1.0) total:0.85 (0.78, 0.93) | (R)- methadoneh 1.03 (0.95, 1.10) total:0.94 (0.87, 1.02) | (R)- methadoneh 1.11 (1.02, 1.20) total:1.02 (0.93, 1.12)
nevirapinei,j | 200 mg BID, d 1–23 (n=23) | 300 mg QD/ritonavir 100 mg QD, d 4–13, then 400 mg QD/ritonavir 100 mg QD, d 14–23 (n=23) | 1.17 (1.09, 1.25) 1.21 (1.11, 1.32) | 1.25 (1.17, 1.34) 1.26 (1.17, 1.36) | 1.32 (1.22, 1.43) 1.35 (1.25, 1.47)
omeprazolek | 40 mg single dose, d 7 and d 20 (n=16) | 400 mg QD, d 1−12 (n=16) | 1.24 (1.04, 1.47) | 1.45 (1.20, 1.76) | NA
rifabutin | 300 mg QD, d 1−10 then 150 mg QD, d 11−20 (n=3) | 600 mg QD,l d 11−20 (n=3) | 1.18 (0.94, 1.48) 25-O- desacetyl- rifabutin: 8.20 (5.90, 11.40) | 2.10 (1.57, 2.79) 25-O- desacetyl- rifabutin: 22.01 (15.97, 30.34) | 3.43 (1.98, 5.96) 25-O- desacetyl- rifabutin: 75.6 (30.1, 190.0)
 | 150 mg twice weekly, d 1−15 (n=7) | 300 mg QD/ritonavir 100 mg QD, d 1−17 (n=7) | 2.49m (2.03, 3.06) 25-O- desacetyl- rifabutin: 7.77 (6.13, 9.83) | 1.48m (1.19, 1.84) 25-O- desacetyl- rifabutin: 10.90 (8.14, 14.61) | 1.40m (1.05, 1.87) 25-O- desacetyl- rifabutin: 11.45 (8.15, 16.10)
rosiglitazonen | 4 mg single dose, d 1, 7, 17 (n=14) | 400 mg QD, d 2–7, then 300 mg QD/ritonavir 100 mg QD, d 8–17 (n=14) | 1.08 (1.03, 1.13) 0.97 (0.91, 1.04) | 1.35 (1.26, 1.44) 0.83 (0.77, 0.89) | NA NA
saquinaviro (soft gelatin capsules) | 1200 mg QD, d 1−13 (n=7) | 400 mg QD, d 7−13 (n=7) | 4.39 (3.24, 5.95) | 5.49 (4.04, 7.47) | 6.86 (5.29, 8.91)
tenofovirp | 300 mg QD, d 9−16 (n=33) and d 24−30 (n=33) | 400 mg QD, d 2−16 (n=33) | 1.14 (1.08, 1.20) | 1.24 (1.21, 1.28) | 1.22 (1.15, 1.30)
 | 300 mg QD, d 1−7 (pm) (n=14) d 25−34 (pm) (n=12) | 300 mg QD/ritonavir 100 mg QD, d 25−34 (am) (n=12)q | 1.34 (1.20, 1.51) | 1.37 (1.30, 1.45) | 1.29 (1.21, 1.36)
lamivudine + zidovudine | 150 mg lamivudine + 300 mg zidovudine BID, d 1−12 (n=19) | 400 mg QD, d 7−12 (n=19) | lamivudine: 1.04 (0.92, 1.16) zidovudine: 1.05 (0.88, 1.24) zidovudine glucuronide: 0.95 (0.88, 1.02) | lamivudine: 1.03 (0.98, 1.08) zidovudine: 1.05 (0.96, 1.14) zidovudine glucuronide: 1.00 (0.97, 1.03) | lamivudine: 1.12 (1.04, 1.21) zidovudine: 0.69 (0.57, 0.84) zidovudine glucuronide: 0.82 (0.62, 1.08)
a Data provided are under fed conditions unless otherwise noted.
b All drugs were given under fasted conditions.
c 400 mg ddI EC and REYATAZ were administered together with food on Days 8 and 19.
d Upon further dose normalization of ethinyl estradiol 25 mcg with atazanavir relative to ethinyl estradiol 35 mcg without atazanavir, the ratio of geometric means (90% confidence intervals) for Cmax, AUC, and Cmin were 0.82 (0.73, 0.92), 1.06 (0.95, 1.17), and 1.35 (1.11, 1.63), respectively.
e Upon further dose normalization of ethinyl estradiol 35 mcg with atazanavir/ritonavir relative to ethinyl estradiol 25 mcg without atazanavir/ritonavir, the ratio of geometric means (90% confidence intervals) for Cmax, AUC, and Cmin were 1.17 (1.03, 1.34), 1.13 (1.05, 1.22), and 0.88 (0.77, 1.00), respectively.
f All subjects were on a 28 day lead-in period; one full cycle of Ortho Tri-Cyclen®. Ortho Tri-Cyclen® contains 35 mcg of ethinyl estradiol. Ortho Tri-Cyclen® LO contains 25 mcg of ethinyl estradiol. Results were dose normalized to an ethinyl estradiol dose of 35 mcg.
g 17-deacetyl norgestimate is the active component of norgestimate.
h (R)-methadone is the active isomer of methadone.
i Study was conducted in HIV-infected individuals.
j Subjects were treated with nevirapine prior to study entry.
k Omeprazole was used as a metabolic probe for CYP2C19. Omeprazole was given 2 hours after REYATAZ on Day 7; and was given alone 2 hours after a light meal on Day 20.
l Not the recommended therapeutic dose of atazanavir.
m When compared to rifabutin 150 mg QD alone d1−10 (n=14). Total of Rifabutin + 25-O-desacetyl-rifabutin: AUC 2.19 (1.78, 2.69).
n Rosiglitazone used as a probe substrate for CYP2C8.
o The combination of atazanavir and saquinavir 1200 mg QD produced daily saquinavir exposures similar to the values produced by the standard therapeutic dosing of saquinavir at 1200 mg TID. However, the Cmax is about 79% higher than that for the standard dosing of saquinavir (soft gelatin capsules) alone at 1200 mg TID.
p Note that similar results were observed in a study where administration of tenofovir and REYATAZ was separated by 12 hours.
q Administration of tenofovir and REYATAZ was temporally separated by 12 hours.
NA = not available.

12.4 Microbiology

Mechanism of Action

Atazanavir (ATV) is an azapeptide HIV-1 protease inhibitor (PI). The compound selectively inhibits the virus-specific processing of viral Gag and Gag-Pol polyproteins in HIV-1 infected cells, thus preventing formation of mature virions.

Antiviral Activity in Cell Culture

Atazanavir exhibits anti-HIV-1 activity with a mean 50% effective concentration (EC50) in the absence of human serum of 2 to 5 nM against a variety of laboratory and clinical HIV-1 isolates grown in peripheral blood mononuclear cells, macrophages, CEM-SS cells, and MT-2 cells. ATV has activity against HIV-1 Group M subtype viruses A, B, C, D, AE, AG, F, G, and J isolates in cell culture. ATV has variable activity against HIV-2 isolates (1.9 to 32 nM), with EC50 values above the EC50 values of failure isolates. Two-drug combination antiviral activity studies with ATV showed no antagonism in cell culture with NNRTIs (delavirdine, efavirenz, and nevirapine), PIs (amprenavir, indinavir, lopinavir, nelfinavir, ritonavir, and saquinavir), NRTIs (abacavir, didanosine, emtricitabine, lamivudine, stavudine, tenofovir, zalcitabine, and zidovudine), the HIV-1 fusion inhibitor enfuvirtide, and two compounds used in the treatment of viral hepatitis, adefovir and ribavirin, without enhanced cytotoxicity.

Resistance

In Cell Culture: HIV-1 isolates with a decreased susceptibility to ATV have been selected in cell culture and obtained from patients treated with ATV or atazanavir/ritonavir (ATV/RTV). HIV-1 isolates with 93- to 183-fold reduced susceptibility to ATV from three different viral strains were selected in cell culture by 5 months. The substitutions in these HIV-1 viruses that contributed to ATV resistance include I50L, N88S, I84V, A71V, and M46I. Changes were also observed at the protease cleavage sites following drug selection. Recombinant viruses containing the I50L substitution without other major PI substitutions were growth impaired and displayed increased susceptibility in cell culture to other PIs (amprenavir, indinavir, lopinavir, nelfinavir, ritonavir, and saquinavir). The I50L and I50V substitutions yielded selective resistance to ATV and amprenavir, respectively, and did not appear to be cross-resistant.

Clinical Studies of Treatment-Naive Patients: Comparison of Ritonavir-Boosted REYATAZ vs. Unboosted REYATAZ: Study AI424-089 compared REYATAZ 300 mg once daily with ritonavir 100 mg vs. REYATAZ 400 mg once daily when administered with lamivudine and extended-release stavudine in HIV-infected treatment-naive patients. A summary of the number of virologic failures and virologic failure isolates with ATV resistance in each arm is shown in Table 19.

Table 19: Summary of Virologic Failuresa at Week 96 in Study AI424-089: Comparison of Ritonavir Boosted REYATAZ vs. Unboosted REYATAZ: Randomized Patients
 | REYATAZ 300 mg + ritonavir 100 mg | REYATAZ 400 mg
 | (n=95) | (n=105)
Virologic Failure (≥50 copies/mL) at Week 96 | 15 (16%) | 34 (32%)
Virologic Failure with Genotypes and Phenotypes Data | 5 | 17
Virologic Failure Isolates with ATV-resistance at Week 96 | 0/5 (0%)b | 4/17 (24%)b
Virologic Failure Isolates with I50L Emergence at Week 96c | 0/5 (0%)b | 2/17 (12%)b
Virologic Failure Isolates with Lamivudine Resistance at Week 96 | 2/5 (40%)b | 11/17 (65%)b
a Virologic failure includes patients who were never suppressed through Week 96 and on study at Week 96, had virologic rebound or discontinued due to insufficient viral load response.
b Percentage of Virologic Failure Isolates with genotypic and phenotypic data.
c Mixture of I50I/L emerged in 2 other ATV 400 mg-treated patients. Neither isolate was phenotypically resistant to ATV.

Clinical Studies of Treatment-Naive Patients Receiving REYATAZ 300 mg With Ritonavir 100 mg: In Phase III study AI424-138, an as-treated genotypic and phenotypic analysis was conducted on samples from patients who experienced virologic failure (HIV-1 RNA ≥400 copies/mL) or discontinued before achieving suppression on ATV/RTV (n=39; 9%) and LPV/RTV (n=39; 9%) through 96 weeks of treatment. In the ATV/RTV arm, one of the virologic failure isolates had a 56-fold decrease in ATV susceptibility emerge on therapy with the development of PI resistance-associated substitutions L10F, V32I, K43T, M46I, A71I, G73S, I85I/V, and L90M. The NRTI resistance-associated substitution M184V also emerged on treatment in this isolate conferring emtricitabine resistance. Two ATV/RTV-virologic failure isolates had baseline phenotypic ATV resistance and IAS-defined major PI resistance-associated substitutions at baseline. The 150L substitution emerged on study in one of these failure isolates and was associated with a 17-fold decrease in ATV susceptibility from baseline and the other failure isolate with baseline ATV resistance and PI substitutions (M46M/I and I84I/V) had additional IAS-defined major PI substitutions (V32I, M46I, and I84V) emerge on ATV treatment associated with a 3-fold decrease in ATV susceptibiity from baseline. Five of the treatment failure isolates in the ATV/RTV arm developed phenotypic emtricitabine resistance with the emergence of either the M184I (n=1) or the M184V (n=4) substitution on therapy and none developed phenotypic tenofovir disoproxil resistance. In the LPV/RTV arm, one of the virologic failure patient isolates had a 69-fold decrease in LPV susceptibility emerge on therapy with the development of PI substitutions L10V, V11I, I54V, G73S, and V82A in addition to baseline PI substitutions L10L/I, V32I, I54I/V, A71I, G73G/S, V82V/A, L89V, and L90M. Six LPV/RTV virologic failure isolates developed the M184V substitution and phenotypic emtricitabine resistance and two developed phenotypic tenofovir disoproxil resistance.

Clinical Studies of Treatment-Naive Patients Receiving REYATAZ 400 mg Without Ritonavir: ATV-resistant clinical isolates from treatment-naive patients who experienced virologic failure on REYATAZ 400 mg treatment without ritonavir often developed an I50L substitution (after an average of 50 weeks of ATV therapy), often in combination with an A71V substitution, but also developed one or more other PI substitutions (eg, V32I, L33F, G73S, V82A, I85V, or N88S) with or without the I50L substitution. In treatment-naive patients, viral isolates that developed the I50L substitution, without other major PI substitutions, showed phenotypic resistance to ATV but retained in cell culture susceptibility to other PIs (amprenavir, indinavir, lopinavir, nelfinavir, ritonavir, and saquinavir); however, there are no clinical data available to demonstrate the effect of the I50L substitution on the efficacy of subsequently administered PIs.

Clinical Studies of Treatment-Experienced Patients: In studies of treatment-experienced patients treated with ATV or ATV/RTV, most ATV-resistant isolates from patients who experienced virologic failure developed substitutions that were associated with resistance to multiple PIs and displayed decreased susceptibility to multiple PIs. The most common protease substitutions to develop in the viral isolates of patients who failed treatment with ATV 300 mg once daily and RTV 100 mg once daily (together with tenofovir and an NRTI) included V32I, L33F/V/I, E35D/G, M46I/L, I50L, F53L/V, I54V, A71V/T/I, G73S/T/C, V82A/T/L, I85V, and L89V/Q/M/T. Other substitutions that developed on ATV/RTV treatment including E34K/A/Q, G48V, I84V, N88S/D/T, and L90M occurred in less than 10% of patient isolates. Generally, if multiple PI resistance substitutions were present in the HIV-1 virus of the patient at baseline, ATV resistance developed through substitutions associated with resistance to other PIs and could include the development of the I50L substitution. The I50L substitution has been detected in treatment-experienced patients experiencing virologic failure after long-term treatment. Protease cleavage site changes also emerged on ATV treatment but their presence did not correlate with the level of ATV resistance.

Cross-Resistance

Cross-resistance among PIs has been observed. Baseline phenotypic and genotypic analyses of clinical isolates from ATV clinical trials of PI-experienced patients showed that isolates cross-resistant to multiple PIs were cross-resistant to ATV. Greater than 90% of the isolates with substitutions that included I84V or G48V were resistant to ATV. Greater than 60% of isolates containing L90M, G73S/T/C, A71V/T, I54V, M46I/L, or a change at V82 were resistant to ATV, and 38% of isolates containing a D30N substitution in addition to other changes were resistant to ATV. Isolates resistant to ATV were also cross-resistant to other PIs with >90% of the isolates resistant to indinavir, lopinavir, nelfinavir, ritonavir, and saquinavir, and 80% resistant to amprenavir. In treatment-experienced patients, PI-resistant viral isolates that developed the I50L substitution in addition to other PI resistance-associated substitution were also cross-resistant to other PIs.

Baseline Genotype/Phenotype and Virologic Outcome Analyses

Genotypic and/or phenotypic analysis of baseline virus may aid in determining ATV susceptibility before initiation of ATV/RTV therapy. An association between virologic response at 48 weeks and the number and type of primary PI resistance-associated substitutions detected in baseline HIV-1 isolates from antiretroviral-experienced patients receiving ATV/RTV once daily or lopinavir (LPV)/RTV twice daily in Study AI424-045 is shown in Table 20.

Overall, both the number and type of baseline PI substitutions affected response rates in treatment-experienced patients. In the ATV/RTV group, patients had lower response rates when 3 or more baseline PI substitutions, including a substitution at position 36, 71, 77, 82, or 90, were present compared to patients with 1–2 PI substitutions, including one of these substitutions.

Table 20: HIV RNA Response by Number and Type of Baseline PI Substitution, Antiretroviral-Experienced Patients in Study AI424-045, As-Treated Analysis
Number and Type of Baseline PI Substitutionsa | Virologic Response = HIV RNA <400 copies/mLb
Number and Type of Baseline PI Substitutionsa | ATV/RTV (n=110) | LPV/RTV (n=113)
3 or more primary PI substitutions including:c
D30N | 75% (6/8) | 50% (3/6)
M36I/V | 19% (3/16) | 33% (6/18)
M46I/L/T | 24% (4/17) | 23% (5/22)
I54V/L/T/M/A | 31% (5/16) | 31% (5/16)
A71V/T/I/G | 34% (10/29) | 39% (12/31)
G73S/A/C/T | 14% (1/7) | 38% (3/8)
V77I | 47% (7/15) | 44% (7/16)
V82A/F/T/S/I | 29% (6/21) | 27% (7/26)
I84V/A | 11% (1/9) | 33% (2/6)
N88D | 63% (5/8) | 67% (4/6)
L90M | 10% (2/21) | 44% (11/25)
Number of baseline primary PI substitutionsa
All patients, as-treated | 58% (64/110) | 59% (67/113)
0–2 PI substitutions | 75% (50/67) | 75% (50/67)
3–4 PI substitutions | 41% (14/34) | 43% (12/28)
5 or more PI substitutions | 0% (0/9) | 28% (5/18)
a Primary substitutions include any change at D30, V32, M36, M46, I47, G48, I50, I54, A71, G73, V77, V82, I84, N88, and L90.
b Results should be interpreted with caution because the subgroups were small.
c There were insufficient data (n<3) for PI substitutions V32I, I47V, G48V, I50V, and F53L.

The response rates of antiretroviral-experienced patients in Study AI424-045 were analyzed by baseline phenotype (shift in susceptibility in cell culture relative to reference, Table 21). The analyses are based on a select patient population with 62% of patients receiving an NNRTI-based regimen before study entry compared to 35% receiving a PI-based regimen. Additional data are needed to determine clinically relevant break points for REYATAZ.

Table 21: Baseline Phenotype by Outcome, Antiretroviral-Experienced Patients in Study AI424-045, As-Treated Analysis
Baseline Phenotypea | Virologic Response = HIV RNA <400 copies/mLb
Baseline Phenotypea | ATV/RTV (n=111) | LPV/RTV (n=111)
0–2 | 71% (55/78) | 70% (56/80)
>2–5 | 53% (8/15) | 44% (4/9)
>5–10 | 13% (1/8) | 33% (3/9)
>10 | 10% (1/10) | 23% (3/13)
a Fold change susceptibility in cell culture relative to the wild-type reference.
b Results should be interpreted with caution because the subgroups were small.

13 NONCLINICAL TOXICOLOGY

13.1 Carcinogenesis, Mutagenesis, Impairment of Fertility

Carcinogenesis

Long-term carcinogenicity studies in mice and rats were carried out with atazanavir for two years. In the mouse study, drug-related increases in hepatocellular adenomas were found in females at 360 mg/kg/day. The systemic drug exposure (AUC) at the NOAEL (no observable adverse effect level) in females, (120 mg/kg/day) was 2.8 times and in males (80 mg/kg/day) was 2.9 times higher than those in humans at the clinical dose (300 mg/day atazanavir boosted with 100 mg/day ritonavir, non-pregnant patients). In the rat study, no drug-related increases in tumor incidence were observed at doses up to 1200 mg/kg/day, for which AUCs were 1.1 (males) or 3.9 (females) times those measured in humans at the clinical dose.

Mutagenesis

Atazanavir tested positive in an in vitro clastogenicity test using primary human lymphocytes, in the absence and presence of metabolic activation. Atazanavir tested negative in the in vitro Ames reverse-mutation assay, in vivo micronucleus and DNA repair tests in rats, and in vivo DNA damage test in rat duodenum (comet assay).

Impairment of Fertility

At the systemic drug exposure levels (AUC) 0.9 (in male rats) or 2.3 (in female rats) times that of the human clinical dose, (300 mg/day atazanavir boosted with 100 mg/day ritonavir) significant effects on mating, fertility, or early embryonic development were not observed.

14 CLINICAL STUDIES

14.1 Adult Patients Without Prior Antiretroviral Therapy

Study AI424-138: a 96-week study comparing the antiviral efficacy and safety of atazanavir/ritonavir with lopinavir/ritonavir, each in combination with fixed-dose tenofovir-emtricitabine in HIV-1 infected treatment-naive subjects. Study AI424-138 is a 96-week open-label, randomized, multicenter study, comparing REYATAZ (300 mg once daily) with ritonavir (100 mg once daily) to lopinavir with ritonavir (400/100 mg twice daily), each in combination with fixed-dose tenofovir with emtricitabine (300/200 mg once daily), in 878 antiretroviral treatment-naive treated patients. Patients had a mean age of 36 years (range: 19–72), 49% were Caucasian, 18% Black, 9% Asian, 23% Hispanic/Mestizo/mixed race, and 68% were male. The median baseline plasma CD4+ cell count was 204 cells/mm^3 (range: 2 to 810 cells/mm^3) and the mean baseline plasma HIV-1 RNA level was 4.94 log10 copies/mL (range: 2.60 to 5.88 log10 copies/mL). Treatment response and outcomes through Week 96 are presented in Table 22.

Table 22: Outcomes of Treatment Through Week 96 (Study AI424-138)
Outcome | REYATAZ 300 mg + ritonavir 100 mg (once daily) with tenofovir/emtricitabine (once daily)a (n=441) | lopinavir 400 mg + ritonavir 100 mg (twice daily) with tenofovir/emtricitabine (once daily)a (n=437)
Outcome | 96 Weeks | 96 Weeks
Responderb,c,d | 75% | 68%
Virologic failuree | 17% | 19%
Rebound | 8% | 10%
Never suppressed through Week 96 | 9% | 9%
Death | 1% | 1%
Discontinued due to adverse event | 3% | 5%
Discontinued for other reasonsf | 4% | 7%
a As a fixed-dose combination: 300 mg tenofovir, 200 mg emtricitabine once daily.
b Patients achieved HIV RNA <50 copies/mL at Week 96. Roche Amplicor®, v1.5 ultra-sensitive assay.
c Pre-specified ITT analysis at Week 48 using as-randomized cohort: ATV/RTV 78% and LPV/RTV 76% [difference estimate: 1.7% (95% confidence interval: −3.8%, 7.1%)].
d Pre-specified ITT analysis at Week 96 using as-randomized cohort: ATV/RTV 74% and LPV/RTV 68% [difference estimate: 6.1% (95% confidence interval: 0.3%, 12.0%)].
e Includes viral rebound and failure to achieve confirmed HIV RNA <50 copies/mL through Week 96.
f Includes lost to follow-up, patient’s withdrawal, noncompliance, protocol violation, and other reasons.

Through 96 weeks of therapy, the proportion of responders among patients with high viral loads (ie, baseline HIV RNA ≥100,000 copies/mL) was comparable for the REYATAZ/ritonavir (165 of 223 patients, 74%) and lopinavir/ritonavir (148 of 222 patients, 67%) arms. At 96 weeks, the median increase from baseline in CD4+ cell count was 261 cells/mm^3 for the REYATAZ/ritonavir arm and 273 cells/mm^3 for the lopinavir/ritonavir arm.

Study AI424-034: REYATAZ once daily compared to efavirenz once daily, each in combination with fixed-dose lamivudine + zidovudine twice daily. Study AI424-034 was a randomized, double-blind, multicenter trial comparing REYATAZ (400 mg once daily) to efavirenz (600 mg once daily), each in combination with a fixed-dose combination of lamivudine (3TC) (150 mg) and zidovudine (ZDV) (300 mg) given twice daily, in 810 antiretroviral treatment-naive patients. Patients had a mean age of 34 years (range: 18 to 73), 36% were Hispanic, 33% were Caucasian, and 65% were male. The mean baseline CD4+ cell count was 321 cells/mm^3 (range: 64 to 1424 cells/mm^3) and the mean baseline plasma HIV-1 RNA level was 4.8 log10 copies/mL (range: 2.2 to 5.9 log10 copies/mL). Treatment response and outcomes through Week 48 are presented in Table 23.

Table 23: Outcomes of Randomized Treatment Through Week 48 (Study AI424-034)
Outcome | REYATAZ 400 mg once daily + lamivudine + zidovudined | efavirenz 600 mg once daily + lamivudine + zidovudined
Outcome | (n=405) | (n=405)
Respondera | 67% (32%) | 62% (37%)
Virologic failureb | 20% | 21%
Rebound | 17% | 16%
Never suppressed through Week 48 | 3% | 5%
Death | – | <1%
Discontinued due to adverse event | 5% | 7%
Discontinued for other reasonsc | 8% | 10%
a Patients achieved and maintained confirmed HIV RNA <400 copies/mL (<50 copies/mL) through Week 48. Roche Amplicor® HIV-1 Monitor™ Assay, test version 1.0 or 1.5 as geographically appropriate.
b Includes viral rebound and failure to achieve confirmed HIV RNA <400 copies/mL through Week 48.
c Includes lost to follow-up, patient’s withdrawal, noncompliance, protocol violation, and other reasons.
d As a fixed-dose combination: 150 mg lamivudine, 300 mg zidovudine twice daily.

Through 48 weeks of therapy, the proportion of responders among patients with high viral loads (ie, baseline HIV RNA ≥100,000 copies/mL) was comparable for the REYATAZ and efavirenz arms. The mean increase from baseline in CD4+ cell count was 176 cells/mm^3 for the REYATAZ arm and 160 cells/mm^3 for the efavirenz arm.

Study AI424-008: REYATAZ 400 mg once daily compared to REYATAZ 600 mg once daily, and compared to nelfinavir 1250 mg twice daily, each in combination with stavudine and lamivudine twice daily. Study AI424-008 was a 48-week, randomized, multicenter trial, blinded to dose of REYATAZ, comparing REYATAZ at two dose levels (400 mg and 600 mg once daily) to nelfinavir (1250 mg twice daily), each in combination with stavudine (40 mg) and lamivudine (150 mg) given twice daily, in 467 antiretroviral treatment-naive patients. Patients had a mean age of 35 years (range: 18 to 69), 55% were Caucasian, and 63% were male. The mean baseline CD4+ cell count was 295 cells/mm^3 (range: 4 to 1003 cells/mm^3) and the mean baseline plasma HIV-1 RNA level was 4.7 log10 copies/mL (range: 1.8 to 5.9 log10 copies/mL). Treatment response and outcomes through Week 48 are presented in Table 24.

Table 24: Outcomes of Randomized Treatment Through Week 48 (Study AI424-008)
Outcome | REYATAZ 400 mg once daily + lamivudine + stavudine (n=181) | nelfinavir 1250 mg twice daily + lamivudine + stavudine (n=91)
Respondera | 67% (33%) | 59% (38%)
Virologic failureb | 24% | 27%
Rebound | 14% | 14%
Never suppressed through Week 48 | 10% | 13%
Death | <1% | –
Discontinued due to adverse event | 1% | 3%
Discontinued for other reasonsc | 7% | 10%
a Patients achieved and maintained confirmed HIV RNA <400 copies/mL (<50 copies/mL) through Week 48. Roche Amplicor® HIV-1 Monitor™ Assay, test version 1.0 or 1.5 as geographically appropriate.
b Includes viral rebound and failure to achieve confirmed HIV RNA <400 copies/mL through Week 48.
c Includes lost to follow-up, patient’s withdrawal, noncompliance, protocol violation, and other reasons.

Through 48 weeks of therapy, the mean increase from baseline in CD4+ cell count was 234 cells/mm^3 for the REYATAZ 400-mg arm and 211 cells/mm^3 for the nelfinavir arm.

14.2 Adult Patients With Prior Antiretroviral Therapy

Study AI424-045: REYATAZ once daily + ritonavir once daily compared to REYATAZ once daily + saquinavir (soft gelatin capsules) once daily, and compared to lopinavir + ritonavir twice daily, each in combination with tenofovir + one NRTI. Study AI424-045 is an ongoing, randomized, multicenter trial comparing REYATAZ (300 mg once daily) with ritonavir (100 mg once daily) to REYATAZ (400 mg once daily) with saquinavir soft gelatin capsules (1200 mg once daily), and to lopinavir + ritonavir (400/100 mg twice daily), each in combination with tenofovir and one NRTI, in 347 (of 358 randomized) patients who experienced virologic failure on HAART regimens containing PIs, NRTIs, and NNRTIs. The mean time of prior exposure to antiretrovirals was 139 weeks for PIs, 283 weeks for NRTIs, and 85 weeks for NNRTIs. The mean age was 41 years (range: 24 to 74); 60% were Caucasian, and 78% were male. The mean baseline CD4+ cell count was 338 cells/mm^3 (range: 14 to 1543 cells/mm^3) and the mean baseline plasma HIV-1 RNA level was 4.4 log10 copies/mL (range: 2.6 to 5.88 log10 copies/mL).

Treatment outcomes through Week 48 for the REYATAZ/ritonavir and lopinavir/ritonavir treatment arms are presented in Table 25. REYATAZ/ritonavir and lopinavir/ritonavir were similar for the primary efficacy outcome measure of time-averaged difference in change from baseline in HIV RNA level. Study AI424-045 was not large enough to reach a definitive conclusion that REYATAZ/ritonavir and lopinavir/ritonavir are equivalent on the secondary efficacy outcome measure of proportions below the HIV RNA lower limit of detection. [See Clinical Pharmacology, Tables 20 and 21 (12.4).]

Table 25: Outcomes of Treatment Through Week 48 in Study AI424-045 (Patients with Prior Antiretroviral Experience)
Outcome | REYATAZ 300 mg + ritonavir 100 mg once daily + tenofovir + 1 NRTI | lopinavir/ritonavir (400/100 mg) twice daily + tenofovir + 1 NRTI | Differencea (REYATAZ-lopinavir/ritonavir)
Outcome | (n=119) | (n=118) | (CI)
HIV RNA Change from Baseline (log10 copies/mL)b | −1.58 | −1.70 | +0.12c (−0.17, 0.41)
CD4+ Change from Baseline (cells/mm^3)d | 116 | 123 | −7 (−67, 52)
Percent of Patients Respondinge
HIV RNA <400 copies/mLb | 55% | 57% | -2.2% (−14.8%, 10.5%)
HIV RNA <50 copies/mLb | 38% | 45% | −7.1% (−19.6%, 5.4%)
a Time-averaged difference through Week 48 for HIV RNA; Week 48 difference in HIV RNA percentages and CD4+ mean changes, REYATAZ/ritonavir vs lopinavir/ritonavir; CI = 97.5% confidence interval for change in HIV RNA; 95% confidence interval otherwise.
b Roche Amplicor® HIV-1 Monitor™ Assay, test version 1.5.
c Protocol-defined primary efficacy outcome measure.
d Based on patients with baseline and Week 48 CD4+ cell count measurements (REYATAZ/ritonavir, n=85; lopinavir/ritonavir, n=93).
e Patients achieved and maintained confirmed HIV-1 RNA <400 copies/mL (<50 copies/mL) through Week 48.

No patients in the REYATAZ/ritonavir treatment arm and three patients in the lopinavir/ritonavir treatment arm experienced a new-onset CDC Category C event during the study.

In Study AI424-045, the mean change from baseline in plasma HIV-1 RNA for REYATAZ 400 mg with saquinavir (n=115) was −1.55 log10 copies/mL, and the time-averaged difference in change in HIV-1 RNA levels versus lopinavir/ritonavir was 0.33. The corresponding mean increase in CD4+ cell count was 72 cells/mm^3. Through 48 weeks of treatment, the proportion of patients in this treatment arm with plasma HIV-1 RNA <400 (<50) copies/mL was 38% (26%). In this study, coadministration of REYATAZ and saquinavir did not provide adequate efficacy [see Drug Interactions (7)].

Study AI424-045 also compared changes from baseline in lipid values. [See Adverse Reactions (6.1).]

Study AI424-043: Study AI424-043 was a randomized, open-label, multicenter trial comparing REYATAZ (400 mg once daily) to lopinavir/ritonavir (400/100 mg twice daily), each in combination with two NRTIs, in 300 patients who experienced virologic failure to only one prior PI-containing regimen. Through 48 weeks, the proportion of patients with plasma HIV-1 RNA <400 (<50) copies/mL was 49% (35%) for patients randomized to REYATAZ (n=144) and 69% (53%) for patients randomized to lopinavir/ritonavir (n=146). The mean change from baseline was −1.59 log10 copies/mL in the REYATAZ treatment arm and −2.02 log10 copies/mL in the lopinavir/ritonavir arm. Based on the results of this study, REYATAZ without ritonavir is inferior to lopinavir/ritonavir in PI-experienced patients with prior virologic failure and is not recommended for such patients.

14.3 Pediatric Patients

Assessment of the pharmacokinetics, safety, tolerability, and efficacy of REYATAZ is based on data from the open-label, multicenter clinical trial PACTG 1020A conducted in patients from 3 months to 21 years of age. In this study, 193 patients (86 antiretroviral-naive and 107 antiretroviral-experienced) received once daily REYATAZ, with or without ritonavir, in combination with two NRTIs.

One-hundred and five patients (6 to less than 18 years of age) treated with the REYATAZ capsule formulation, with or without ritonavir, were evaluated. Using an ITT analysis, the overall proportions of antiretroviral-naive and -experienced patients with HIV RNA <400 copies/mL at Week 96 were 51% (22/43) and 34% (21/62), respectively. The overall proportions of antiretroviral-naive and -experienced patients with HIV RNA <50 copies/mL at Week 96 were 47% (20/43) and 24% (15/62), respectively. The median increase from baseline in absolute CD4 count at 96 weeks of therapy was 335 cells/mm^3 in antiretroviral-naive patients and 220 cells/mm^3 in antiretroviral-experienced patients.

16 HOW SUPPLIED/STORAGE AND HANDLING

REYATAZ® (atazanavir sulfate) Capsules are available in the following strengths and configurations of plastic bottles with child-resistant closures.

Product Strength* | Capsule Shell Color (cap/body) | Markings on Capsule (ink color) |  | Capsules per Bottle | NDC Number
cap | body
150 mg | blue/powder blue | BMS 150 mg (white) | 3624 (blue) | 60 | 54868-4857-0
300 mg | red/blue | BMS 300 mg (white) | 3622 (white) | 30 | 54868-5838-0

* atazanavir equivalent as atazanavir sulfate.

REYATAZ (atazanavir sulfate) Capsules should be stored at 25° C (77° F); excursions permitted to 15–30° C (59–86° F) [see USP Controlled Room Temperature].

17 PATIENT COUNSELING INFORMATION

See FDA-approved patient labeling (Patient Information).

A statement to patients and healthcare providers is included on the product’s bottle label: ALERT: Find out about medicines that should NOT be taken with REYATAZ.

Patients should be informed that REYATAZ is not a cure for HIV infection and that they may continue to develop opportunistic infections and other complications associated with HIV disease. Patients should be told that there are currently no data demonstrating that therapy with REYATAZ can reduce the risk of transmitting HIV to others through sexual contact.

17.1 Dosing Instructions

Patients should be told that sustained decreases in plasma HIV RNA have been associated with a reduced risk of progression to AIDS and death. Patients should remain under the care of a physician while using REYATAZ. Patients should be advised to take REYATAZ with food every day and take other concomitant antiretroviral therapy as prescribed. REYATAZ must always be used in combination with other antiretroviral drugs. Patients should not alter the dose or discontinue therapy without consulting with their doctor. If a dose of REYATAZ is missed, patients should take the dose as soon as possible and then return to their normal schedule. However, if a dose is skipped the patient should not double the next dose.

17.2 Drug Interactions

REYATAZ may interact with some drugs; therefore, patients should be advised to report to their doctor the use of any other prescription, nonprescription medication, or herbal products, particularly St. John’s wort.

Patients receiving a PDE5 inhibitor and atazanavir should be advised that they may be at an increased risk of PDE5 inhibitor-associated adverse events including hypotension, syncope, visual disturbances, and priapism, and should promptly report any symptoms to their doctor.

Patients should be informed that REVATIO® (used to treat pulmonary arterial hypertension) is contraindicated with REYATAZ and that dose adjustments are necessary when REYATAZ is used with CIALIS®, LEVITRA® or VIAGRA® (used to treat erectile dysfunction), or ADCIRCA® (used to treat pulmonary arterial hypertension).

17.3 Cardiac Conduction Abnormalities

Patients should be informed that atazanavir may produce changes in the electrocardiogram (eg, PR prolongation). Patients should consult their physician if they are experiencing symptoms such as dizziness or lightheadedness.

17.4 Rash

Patients should be informed that mild rashes without other symptoms have been reported with REYATAZ use. These rashes go away within two weeks with no change in treatment. However, there have been a few reports of severe skin reactions (eg, Stevens-Johnson syndrome, erythema multiforme, and toxic skin eruptions) with REYATAZ use. Patients developing signs or symptoms of severe skin reactions or hypersensitivity reactions (including, but not limited to, severe rash or rash accompanied by one or more of the following: fever, general malaise, muscle or joint aches, blisters, oral lesions, conjunctivitis, facial edema, hepatitis, eosinophilia, granulocytopenia, lymphadenopathy, and renal dysfunction) must discontinue REYATAZ and seek medical evaluation immediately.

17.5 Hyperbilirubinemia

Patients should be informed that asymptomatic elevations in indirect bilirubin have occurred in patients receiving REYATAZ. This may be accompanied by yellowing of the skin or whites of the eyes and alternative antiretroviral therapy may be considered if the patient has cosmetic concerns.

17.6 Fat Redistribution

Patients should be informed that redistribution or accumulation of body fat may occur in patients receiving antiretroviral therapy including protease inhibitors and that the cause and long-term health effects of these conditions are not known at this time. It is unknown whether long-term use of REYATAZ will result in a lower incidence of lipodystrophy than with other protease inhibitors.

PATIENT INFORMATION

Patient Information

REYATAZ® (RAY-ah-taz)

(generic name = atazanavir sulfate)

Capsules

ALERT: Find out about medicines that should NOT be taken with REYATAZ. Read the section “What important information should I know about taking REYATAZ with other medicines?”

Read the Patient Information that comes with REYATAZ before you start using it and each time you get a refill. There may be new information. This leaflet provides a summary about REYATAZ and does not include everything there is to know about your medicine. This information does not take the place of talking with your healthcare provider about your medical condition or treatment.

What is REYATAZ?

REYATAZ is a prescription medicine used with other anti-HIV medicines to treat people 6 years of age and older who are infected with the human immunodeficiency virus (HIV). HIV is the virus that causes acquired immune deficiency syndrome (AIDS). REYATAZ is a type of anti-HIV medicine called a protease inhibitor. HIV infection destroys CD4+ (T) cells, which are important to the immune system. The immune system helps fight infection. After a large number of (T) cells are destroyed, AIDS develops. REYATAZ helps to block HIV protease, an enzyme that is needed for the HIV virus to multiply. REYATAZ may lower the amount of HIV in your blood, help your body keep its supply of CD4+ (T) cells, and reduce the risk of death and illness associated with HIV.

Does REYATAZ cure HIV or AIDS?

REYATAZ does not cure HIV infection or AIDS. At present there is no cure for HIV infection. People taking REYATAZ may still get opportunistic infections or other conditions that happen with HIV infection. Opportunistic infections are infections that develop because the immune system is weak. Some of these conditions are pneumonia, herpes virus infections, and Mycobacterium avium complex (MAC) infections. It is very important that you see your healthcare provider regularly while taking REYATAZ.

REYATAZ does not lower your chance of passing HIV to other people through sexual contact, sharing needles, or being exposed to your blood. For your health and the health of others, it is important to always practice safer sex by using a latex or polyurethane condom or other barrier to lower the chance of sexual contact with semen, vaginal secretions, or blood. Never use or share dirty needles.

Who should not take REYATAZ?

Do not take REYATAZ if you:

- are taking certain medicines. (See “What important information should I know about taking REYATAZ with other medicines?”) Serious life-threatening side effects or death may happen. Before you take REYATAZ, tell your healthcare provider about all medicines you are taking or planning to take. These include other prescription and nonprescription medicines, vitamins, and herbal supplements.
- are allergic to REYATAZ or to any of its ingredients. The active ingredient is atazanavir sulfate. See the end of this leaflet for a complete list of ingredients in REYATAZ. Tell your healthcare provider if you think you have had an allergic reaction to any of these ingredients.

What should I tell my healthcare provider before I take REYATAZ?

Tell your healthcare provider:

- If you are pregnant or plan to become pregnant. REYATAZ use during pregnancy has not been associated with an increase in birth defects. Pregnant women have experienced serious side effects when taking REYATAZ with other HIV medicines called nucleoside analogues. You and your healthcare provider will need to decide if REYATAZ is right for you. If you use REYATAZ while you are pregnant, talk to your healthcare provider about the Antiretroviral Pregnancy Registry.
  - After your baby is born, tell your healthcare provider if your baby’s skin or the white part of his/her eyes turns yellow.
- If you are breast-feeding. You should not breast-feed if you are HIV-positive because of the chance of passing HIV to your baby. Also, it is not known if REYATAZ can pass into your breast milk and if it can harm your baby. If you are a woman who has or will have a baby, talk with your healthcare provider about the best way to feed your baby.
- If you have liver problems or are infected with the hepatitis B or C virus. See “What are the possible side effects of REYATAZ?”
- If you have end stage kidney disease managed with hemodialysis.
- If you have diabetes. See “What are the possible side effects of REYATAZ?”
- If you have hemophilia. See “What are the possible side effects of REYATAZ?”
- About all the medicines you take including prescription and nonprescription medicines, vitamins, and herbal supplements. Keep a list of your medicines with you to show your healthcare provider. For more information, see “What important information should I know about taking REYATAZ with other medicines?” and “Who should not take REYATAZ?” Some medicines can cause serious side effects if taken with REYATAZ.

How should I take REYATAZ?

- Take REYATAZ once every day exactly as instructed by your healthcare provider.
  Your healthcare provider will prescribe the amount of REYATAZ that is right for you.
- Always take REYATAZ with food (a meal or snack) to help it work better. Swallow the capsules whole. Do not open the capsules. Take REYATAZ at the same time each day.
- If you are taking antacids or didanosine (VIDEX® or VIDEX® EC), take REYATAZ 2 hours before or 1 hour after these medicines.
- If you are taking medicines for indigestion, heartburn, or ulcers such as AXID® (nizatidine), PEPCID AC® (famotidine), TAGAMET® (cimetidine), ZANTAC® (ranitidine), AcipHex® (rabeprazole), NEXIUM® (esomeprazole), PREVACID® (lansoprazole), PRILOSEC® (omeprazole), or PROTONIX® (pantoprazole), talk to your healthcare provider.
- Do not change your dose or stop taking REYATAZ without first talking with your healthcare provider. It is important to stay under a healthcare provider’s care while taking REYATAZ.
- When your supply of REYATAZ starts to run low, get more from your healthcare provider or pharmacy. It is important not to run out of REYATAZ. The amount of HIV in your blood may increase if the medicine is stopped for even a short time.
- If you miss a dose of REYATAZ, take it as soon as possible and then take your next scheduled dose at its regular time. If, however, it is within 6 hours of your next dose, do not take the missed dose. Wait and take the next dose at the regular time. Do not double the next dose. It is important that you do not miss any doses of REYATAZ or your other anti-HIV medicines.
- If you take more than the prescribed dose of REYATAZ, call your healthcare provider or poison control center right away.

What are the possible side effects of REYATAZ?

The following list of side effects is not complete. Report any new or continuing symptoms to your healthcare provider. If you have questions about side effects, ask your healthcare provider. Your healthcare provider may be able to help you manage these side effects.

The following side effects have been reported with REYATAZ:

- mild rash (redness and itching) without other symptoms sometimes occurs in patients taking REYATAZ, most often in the first few weeks after the medicine is started. Rashes usually go away within 2 weeks with no change in treatment. Tell your healthcare provider if rash occurs.
- severe rash: Rash may develop in association with other symptoms which could be serious and potentially cause death.
  If you develop a rash with any of the following symptoms stop using REYATAZ and call your healthcare provider right away:
  - shortness of breath
  - general ill feeling or “flu-like” symptoms
  - fever
  - muscle or joint aches
  - conjunctivitis (red or inflamed eyes, like “pink eye”)
  - blisters
  - mouth sores
  - swelling of your face
- yellowing of the skin or eyes. These effects may be due to increases in bilirubin levels in the blood (bilirubin is made by the liver). Although these effects may not be damaging to your liver, skin, or eyes, call your healthcare provider promptly if your skin or the white part of your eyes turn yellow.
- a change in the way your heart beats (heart rhythm change). Call your healthcare provider right away if you get dizzy or lightheaded. These could be symptoms of a heart problem.
- diabetes and high blood sugar (hyperglycemia) sometimes happen in patients taking protease inhibitor medicines like REYATAZ. Some patients had diabetes before taking protease inhibitors while others did not. Some patients may need changes in their diabetes medicine.
- if you have liver disease including hepatitis B or C, your liver disease may get worse when you take anti-HIV medicines like REYATAZ.
- kidney stones have been reported in patients taking REYATAZ. If you develop signs or symptoms of kidney stones (pain in your side, blood in your urine, pain when you urinate) tell your healthcare provider promptly.
- some patients with hemophilia have increased bleeding problems with protease inhibitors like REYATAZ.
- changes in body fat. These changes may include an increased amount of fat in the upper back and neck (“buffalo hump”), breast, and around the trunk. Loss of fat from the legs, arms, and face may also happen. The cause and long-term health effects of these conditions are not known at this time.
- immune reconstitution syndrome. In some patients with advanced HIV infection (AIDS) and a history of opportunistic infection, signs and symptoms of inflammation from previous infections may occur soon after anti-HIV treatment, including REYATAZ, is started.

Other common side effects of REYATAZ taken with other anti-HIV medicines include nausea; headache; stomach pain; vomiting; diarrhea; depression; fever; dizziness; trouble sleeping; numbness, tingling, or burning of hands or feet; and muscle pain.

Gallbladder disorders (which may include gallstones and gallbladder inflammation) have been reported in patients taking REYATAZ.

What important information should I know about taking REYATAZ with other medicines?

Do not take REYATAZ if you take the following medicines (not all brands may be listed; tell your healthcare provider about all the medicines you take). REYATAZ may cause serious, life-threatening side effects or death when used with these medicines.

- Ergot medicines: dihydroergotamine, ergonovine, ergotamine, and methylergonovine such as CAFERGOT®, MIGRANAL®, D.H.E. 45®, ergotrate maleate, METHERGINE®, and others (used for migraine headaches).
- ORAP® (pimozide, used for Tourette’s disorder).
- PROPULSID® (cisapride, used for certain stomach problems).
- Triazolam, also known as HALCION® (used for insomnia).
- Midazolam, also known as VERSED® (used for sedation), when taken by mouth.

Do not take the following medicines with REYATAZ because of possible serious side effects:

- CAMPTOSAR® (irinotecan, used for cancer).
- CRIXIVAN® (indinavir, used for HIV infection). Both REYATAZ and CRIXIVAN sometimes cause increased levels of bilirubin in the blood.
- Cholesterol-lowering medicines MEVACOR® (lovastatin) or ZOCOR® (simvastatin).
- UROXATRAL® (alfuzosin, used to treat benign enlargement of the prostate).
- REVATIO® (sildenafil, used to treat pulmonary arterial hypertension).

Do not take the following medicines with REYATAZ because they may lower the amount of REYATAZ in your blood. This may lead to an increased HIV viral load. Resistance to REYATAZ or cross-resistance to other HIV medicines may develop:

- Rifampin (also known as RIMACTANE®, RIFADIN®, RIFATER®, or RIFAMATE®, used for tuberculosis).
- St. John’s wort (Hypericum perforatum), an herbal product sold as a dietary supplement, or products containing St. John’s wort.
- VIRAMUNE® (nevirapine, used for HIV infection).

The following medicines are not recommended with REYATAZ:

- SEREVENT DISKUS® (salmeterol) and ADVAIR® (salmeterol with fluticasone), used to treat asthma, emphysema/chronic obstructive pulmonary disease also known as COPD.

Do not take the following medicine if you are taking REYATAZ and NORVIR® together:

- VFEND® (voriconazole).

The following medicines may require your healthcare provider to monitor your therapy more closely (for some medicines a change in the dose or dose schedule may be needed):

- CIALIS® (tadalafil), LEVITRA® (vardenafil), or VIAGRA® (sildenafil), used to treat erectile dysfunction. REYATAZ may increase the chances of serious side effects that can happen with CIALIS, LEVITRA, or VIAGRA. Do not use CIALIS, LEVITRA, or VIAGRA while you are taking REYATAZ unless your healthcare provider tells you it is okay.
- ADCIRCA® (tadalafil) or TRACLEER® (bosentan), used to treat pulmonary arterial hypertension.
- LIPITOR® (atorvastatin) or CRESTOR® (rosuvastatin). There is an increased chance of serious side effects if you take REYATAZ with this cholesterol-lowering medicine.
- Medicines for abnormal heart rhythm: CORDARONE® (amiodarone), lidocaine, quinidine (also known as CARDIOQUIN®, QUINIDEX®, and others).
- MYCOBUTIN® (rifabutin, an antibiotic used to treat tuberculosis).
- BUPRENEX®, SUBUTEX®, SUBOXONE® (buprenorphine or buprenorphine/naloxone, used to treat pain and addiction to narcotic painkillers).
- VASCOR® (bepridil, used for chest pain).
- COUMADIN® (warfarin).
- Tricyclic antidepressants such as ELAVIL® (amitriptyline), NORPRAMIN® (desipramine), SINEQUAN® (doxepin), SURMONTIL® (trimipramine), TOFRANIL® (imipramine), or VIVACTIL® (protriptyline).
- Medicines to prevent organ transplant rejection: SANDIMMUNE® or NEORAL® (cyclosporin), RAPAMUNE® (sirolimus), or PROGRAF® (tacrolimus).
- The antidepressant trazodone (DESYREL® and others).
- Fluticasone propionate (FLONASE®, FLOVENT®), given by nose or inhaled to treat allergic symptoms or asthma. Your doctor may choose not to keep you on fluticasone, especially if you are also taking NORVIR®.
- Colchicine (COLCRYS®), used to prevent or treat gout or treat familial Mediterranean fever.

The following medicines may require a change in the dose or dose schedule of either REYATAZ or the other medicine:

- INVIRASE® (saquinavir).
- NORVIR® (ritonavir).
- SUSTIVA® (efavirenz).
- Antacids or buffered medicines.
- VIDEX® (didanosine).
- VIREAD® (tenofovir disoproxil fumarate).
- MYCOBUTIN® (rifabutin).
- Calcium channel blockers such as CARDIZEM® or TIAZAC® (diltiazem), COVERA-HS® or ISOPTIN SR® (verapamil) and others.
- BIAXIN® (clarithromycin).
- Medicines for indigestion, heartburn, or ulcers such as AXID® (nizatidine), PEPCID AC® (famotidine), TAGAMET® (cimetidine), or ZANTAC® (ranitidine).

Talk to your healthcare provider about choosing an effective method of contraception. REYATAZ may affect the safety and effectiveness of hormonal contraceptives such as birth control pills or the contraceptive patch. Hormonal contraceptives do not prevent the spread of HIV to others.

Remember:

1. Know all the medicines you take.
2. Tell your healthcare provider about all the medicines you take.
3. Do not start a new medicine without talking to your healthcare provider.

How should I store REYATAZ?

- Store REYATAZ Capsules at room temperature, 59° to 86° F (15° to 30° C). Do not store this medicine in a damp place such as a bathroom medicine cabinet or near the kitchen sink.
- Keep your medicine in a tightly closed container.
- Keep all medicines out of the reach of children and pets at all times. Do not keep medicine that is out of date or that you no longer need. Dispose of unused medicines through community take-back disposal programs when available or place REYATAZ in an unrecognizable, closed container in the household trash.

General information about REYATAZ

This medicine was prescribed for your particular condition. Do not use REYATAZ for another condition. Do not give REYATAZ to other people, even if they have the same symptoms you have. It may harm them. Keep REYATAZ and all medicines out of the reach of children and pets.

This summary does not include everything there is to know about REYATAZ. Medicines are sometimes prescribed for conditions that are not mentioned in patient information leaflets. Remember no written summary can replace careful discussion with your healthcare provider. If you would like more information, talk with your healthcare provider or you can call 1-800-321-1335.

What are the ingredients in REYATAZ?

Active Ingredient: atazanavir sulfate

Inactive Ingredients: Crospovidone, lactose monohydrate (milk sugar), magnesium stearate, gelatin, FD&C Blue #2, and titanium dioxide.

VIDEX® and REYATAZ® are registered trademarks of Bristol-Myers Squibb Company. COUMADIN® and SUSTIVA® are registered trademarks of Bristol-Myers Squibb Pharma Company. DESYREL® is a registered trademark of Mead Johnson and Company. Other brands listed are the trademarks of their respective owners and are not trademarks of Bristol-Myers Squibb Company.

Bristol-Myers Squibb Company
Princeton, NJ 08543 USA

1246226B0
Rev October 2011

Additional barcode labeling by:

Physicians Total Care, Inc.

Tulsa, Oklahoima 74146

PACKAGE LABEL

REPRESENTATIVE PACKAGING

NDC 54868-4857-0
60 Capsules

REYATAZ®
(atazanavir sulfate)
150 mg

Rx only

Note to pharmacist: Do not cover ALERT box with pharmacy label.
ALERT: Find out about medicines that
should NOT be taken with REYATAZ®

PACKAGE LABEL

REPRESENTATIVE PACKAGING

NDC 54868-5838-0
30 Capsules

REYATAZ®
(atazanavir sulfate)
300 mg

Rx only

Note to pharmacist: Do not cover ALERT box with pharmacy label.
ALERT: Find out about medicines that
should NOT be taken with REYATAZ®